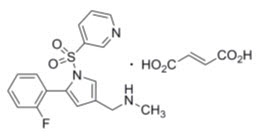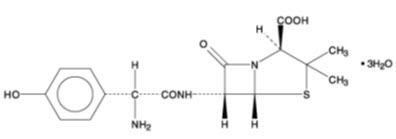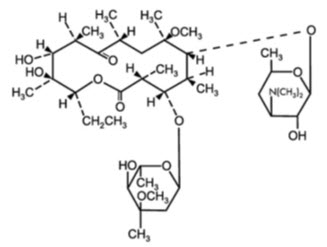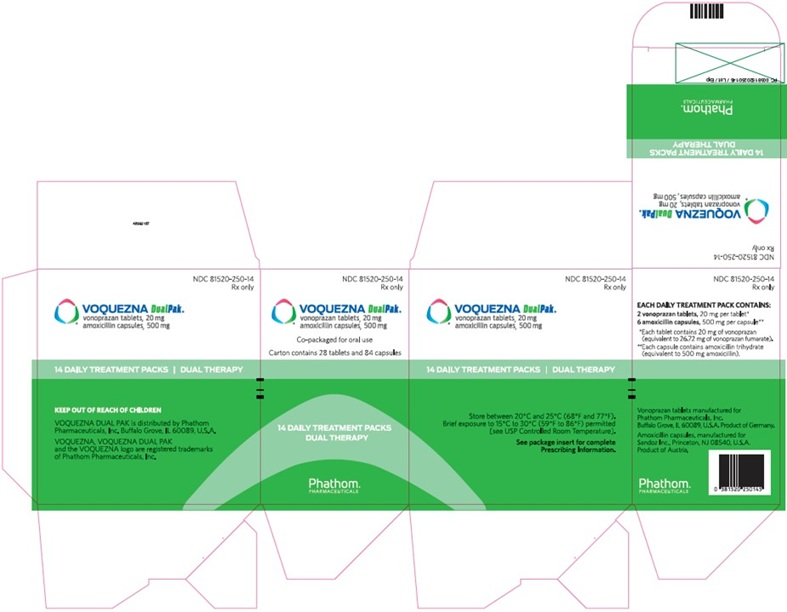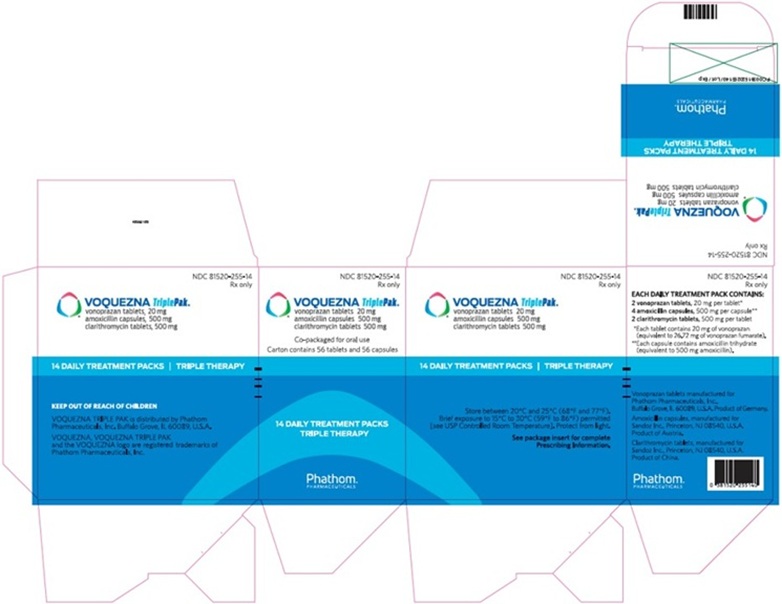 DRUG LABEL: VOQUEZNA DUAL PAK
NDC: 81520-250 | Form: KIT | Route: ORAL
Manufacturer: Phathom Pharmaceuticals Inc.
Category: prescription | Type: HUMAN PRESCRIPTION DRUG LABEL
Date: 20251218

ACTIVE INGREDIENTS: vonoprazan fumarate 26.72 mg/1 1; amoxicillin 500 mg/1 1
INACTIVE INGREDIENTS: Mannitol; Microcrystalline Cellulose; Hydroxypropyl Cellulose, Unspecified; Fumaric Acid; Croscarmellose sodium; Magnesium Stearate; Hypromellose, unspecified; Polyethylene Glycol 8000; Titanium Dioxide; Ferric Oxide Red; Ascorbic acid; Microcrystalline Cellulose; Magnesium Stearate; Ferric Oxide Yellow; Titanium Dioxide; Gelatin, Unspecified; Ferrosoferric Oxide; Shellac; Propylene Glycol; Potassium Hydroxide; Ammonia

HIGHLIGHTS OF PRESCRIBING INFORMATION

These highlights do not include all the information needed to use VOQUEZNA® TRIPLE PAK® and VOQUEZNA® DUAL PAK® safely and effectively. See full prescribing information for VOQUEZNA TRIPLE PAK and VOQUEZNA DUAL PAK.
VOQUEZNA TRIPLE PAK (vonoprazan tablets; amoxicillin capsules; clarithromycin tablets), co-packaged for oral use VOQUEZNA DUAL PAK (vonoprazan tablets; amoxicillin capsules) co-packaged for oral use
Initial U.S. Approval: 2022

1 INDICATIONS AND USAGE

VOQUEZNA TRIPLE PAK, is a co-packaged product containing vonoprazan, a potassium-competitive acid blocker (PCAB), amoxicillin, a penicillin class antibacterial, and clarithromycin, a macrolide antimicrobial, indicated for the treatment of Helicobacter pylori (H. pylori) infection in adults. (1.1)

VOQUEZNA DUAL PAK, is a co-packaged product containing vonoprazan, a PCAB, and amoxicillin, a penicillin class antibacterial, indicated for the treatment of H. pylori infection in adults. (1.1)

To reduce the development of drug-resistant bacteria and maintain the effectiveness of VOQUEZNA TRIPLE PAK, VOQUEZNA DUAL PAK and other antibacterial drugs, VOQUEZNA TRIPLE PAK and VOQUEZNA DUAL PAK should be used only to treat or prevent infections that are proven or strongly suspected to be caused by bacteria. (1.2)

2 DOSAGE AND ADMINISTRATION

VOQUEZNA TRIPLE PAK: The recommended dosage is vonoprazan 20 mg plus amoxicillin 1,000 mg plus clarithromycin 500 mg, each given twice daily (morning and evening, 12 hours apart), with or without food, for 14 days. (2.1)

VOQUEZNA DUAL PAK: The recommended dosage is vonoprazan 20 mg twice daily (morning and evening) plus amoxicillin 1,000 mg, three times a day (morning, mid-day, and evening), with or without food, for 14 days. (2.2)

See full prescribing information for the recommended dosage for patients with renal or hepatic impairment. (2.3, 2.4)

3 DOSAGE FORMS AND STRENGTHS

VOQUEZNA TRIPLE PAK: Carton of 14 daily administration packs for morning and evening dosing, each containing the following three drug products (3.1):

- Tablets: Vonoprazan 20 mg
- Capsules: Amoxicillin 500 mg
- Tablets: Clarithromycin 500 mg

VOQUEZNA DUAL PAK: Carton of 14 daily administration packs for morning, mid-day, and evening dosing, each containing the following two drug products (3.2):

- Tablets: Vonoprazan 20 mg
- Capsules: Amoxicillin 500 mg

4 CONTRAINDICATIONS

VOQUEZNA TRIPLE PAK and VOQUEZNA DUAL PAK:

- Known hypersensitivity to vonoprazan, amoxicillin or any other beta-lactams, clarithromycin or any other macrolide antimicrobial or any component of VOQUEZNA TRIPLE PAK. (4.1)
- Known hypersensitivity to vonoprazan, amoxicillin or any other beta-lactams or any component of VOQUEZNA DUAL PAK. (4.1)
- Rilpivirine-containing products. (4.1)

VOQUEZNA TRIPLE PAK Due to the Clarithromycin Component:

- Pimozide. (4.2)
- Lomitapide, lovastatin, and simvastatin. (4.2)
- Ergot alkaloids (ergotamine or dihydroergotamine). (4.2)
- Colchicine in renal or hepatic impairment. (4.2)
- History of cholestatic jaundice/hepatic dysfunction with use of clarithromycin. (4.2)
- Lurasidone. (4.2)

5 WARNINGS AND PRECAUTIONS

VOQUEZNA TRIPLE PAK and VOQUEZNA DUAL PAK:

- Hypersensitivity Reactions: Serious and occasionally fatal reactions (e.g., anaphylaxis) have been reported with components of VOQUEZNA TRIPLE PAK and VOQUEZNA DUAL PAK. If hypersensitivity reactions occur, discontinue VOQUEZNA TRIPLE PAK or VOQUEZNA DUAL PAK and institute immediate therapy (e.g., anaphylaxis management). (5.1)
- Acute Tubulointerstitial Nephritis: Discontinue VOQUEZNA TRIPLE PAK or VOQUEZNA DUAL PAK and evaluate patients. (5.1)
- Severe Cutaneous Adverse Reactions (SCAR): Discontinue VOQUEZNA TRIPLE PAK or VOQUEZNA DUAL PAK at the first signs or symptoms of SCAR or other signs of hypersensitivity and consider further evaluation. (5.1)
- Drug-induced enterocolitis syndrome (DIES) has been reported with use of amoxicillin, a component of VOQUEZNA TRIPLE PAK and VOQUEZNA DUAL PAK. If this occurs, discontinue VOQUEZNA TRIPLE PAK or VOQUEZNA DUAL PAK and institute appropriate therapy. (5.1)
- Clostridioides difficile-associated diarrhea (CDAD): Evaluate if diarrhea occurs with VOQUEZNA TRIPLE PAK and VOQUEZNA DUAL PAK. (5.1)

VOQUEZNA TRIPLE PAK Due to the Clarithromycin Component:

- QT Prolongation: Avoid VOQUEZNA TRIPLE PAK in patients with known QT prolongation or receiving drugs known to prolong the QT interval, ventricular arrhythmia (torsades de pointes), hypokalemia/hypomagnesemia, significant bradycardia, or taking Class IA or III antiarrhythmics. (5.2)
- Hepatotoxicity: Discontinue if signs and symptoms of hepatitis occur with VOQUEZNA TRIPLE PAK. (5.2)
- Serious Adverse Reactions Due to Concomitant Use with Other Drugs: Serious adverse reactions can occur with VOQUEZNA TRIPLE PAK due to drug interactions of clarithromycin with colchicine, some lipid lowering agents, some calcium channel blockers, and other drugs. (5.2)
- Embryo-Fetal Toxicity: Based on the findings from animal studies and human observational studies in pregnant women treated with clarithromycin, VOQUEZNA TRIPLE PAK is not recommended for use in pregnant women except in clinical circumstances where no alternative therapy is appropriate. (5.2)
- Myasthenia Gravis: Exacerbation of myasthenia gravis can occur with VOQUEZNA TRIPLE PAK since it has been reported in patients receiving clarithromycin tablets. (5.2)

6 ADVERSE REACTIONS

VOQUEZNA TRIPLE PAK: Most common adverse reactions (≥ 2%) were dysgeusia, diarrhea, vulvovaginal candidiasis, headache, abdominal pain, and hypertension. (6.1)

VOQUEZNA DUAL PAK: Most common adverse reactions (≥ 2%) were diarrhea, abdominal pain, vulvovaginal candidiasis, and nasopharyngitis. (6.1)

To report SUSPECTED ADVERSE REACTIONS, contact Phathom Pharmaceuticals, Inc. at toll-free phone 1-888-775-7428 or FDA at 1-800-FDA-1088 or www.fda.gov/medwatch).

7 DRUG INTERACTIONS

Components of VOQUEZNA TRIPLE PAK and VOQUEZNA DUAL PAK have the potential for clinically important drug interactions. See Full Prescribing Information for important drug interactions with VOQUEZNA TRIPLE PAK and VOQUEZNA DUAL PAK. (4, 5.2, 7)

8 USE IN SPECIFIC POPULATIONS

- Geriatrics: VOQUEZNA TRIPLE PAK increased risk of torsades de pointes due to the clarithromycin component. (8.5)
- Renal Impairment: Use is not recommended in severe renal impairment. (8.6)
- Hepatic Impairment: Use is not recommended in moderate and severe hepatic impairment. (8.7)

FULL PRESCRIBING INFORMATION

1 INDICATIONS AND USAGE

1.1 Helicobacter pylori Infection

VOQUEZNA TRIPLE PAK or VOQUEZNA DUAL PAK are indicated for the treatment of Helicobacter pylori (H. pylori) infection in adults [see Clinical Studies (14)].

1.2 Usage

To reduce the development of drug-resistant bacteria and maintain the effectiveness of VOQUEZNA TRIPLE PAK, VOQUEZNA DUAL PAK and other antibacterial drugs, VOQUEZNA TRIPLE PAK and VOQUEZNA DUAL PAK should be used only to treat or prevent infections that are proven or strongly suspected to be caused by susceptible bacteria. When culture and susceptibility information are available, they should be considered in selecting or modifying antibacterial therapy. In the absence of such data, local epidemiology and susceptibility patterns may contribute to the empiric selection of therapy.

2 DOSAGE AND ADMINISTRATION

2.1 Recommended Dosage for VOQUEZNA TRIPLE PAK

VOQUEZNA TRIPLE PAK is a co-packaged product containing vonoprazan tablets, amoxicillin capsules, and clarithromycin tablets each given twice daily (in the morning and evening, 12 hours apart) with or without food, for 14 days [see Clinical Pharmacology (12.3)]. The recommended adult oral dosage of VOQUEZNA TRIPLE PAK is the following:

- In the morning, take 20 mg of vonoprazan (one oval pale red tablet), 1,000 mg of amoxicillin (two yellow capsules), and 500 mg of clarithromycin (one oval white tablet)
- In the evening, take 20 mg of vonoprazan (one oval pale red tablet), and 1,000 mg of amoxicillin (two yellow capsules), and 500 mg of clarithromycin (one oval white tablet)

2.2 Recommended Dosage for VOQUEZNA DUAL PAK

VOQUEZNA DUAL PAK is a co-packaged product containing vonoprazan tablets and amoxicillin capsules given with or without food, for 14 days [see Clinical Pharmacology (12.3)]. The recommended adult oral dosage of VOQUEZNA DUAL PAK is the following:

- In the morning, take 20 mg of vonoprazan (one oval pale red tablet) and 1,000 mg of amoxicillin (two yellow capsules)
- Mid-day, take 1,000 mg of amoxicillin (two yellow capsules)
- In the evening, take 20 mg of vonoprazan (one oval pale red tablet) and 1,000 mg of amoxicillin (two yellow capsules)

2.3 Recommended Dosage in Patients with Renal Impairment

The recommended dosage of VOQUEZNA TRIPLE PAK and VOQUEZNA DUAL PAK in adult patients with renal impairment is described in Table 1 [see Use in Specific Populations (8.6) and Clinical Pharmacology (12.3)].

Table 1: Recommended Dosage of VOQUEZNA TRIPLE PAK and VOQUEZNA DUAL PAK in Patients with Renal Impairment
Estimated GFR | Recommended Dosage
Estimated GFR | VOQUEZNA TRIPLE PAK | VOQUEZNA DUAL PAK
30 mL/minute or greater | 20 mg vonoprazan twice daily 1,000 mg amoxicillin twice daily 500 mg clarithromycin twice daily | 20 mg vonoprazan twice daily 1,000 mg amoxicillin three times daily
Less than 30 mL/minute | Use is not recommended

2.4 Recommended Dosage in Patients with Hepatic Impairment

The recommended dosage of VOQUEZNA TRIPLE PAK and VOQUEZNA DUAL PAK in adult patients with hepatic impairment is described in Table 2 [see Use in Specific Populations (8.7) and Clinical Pharmacology (12.3)].

Table 2: Recommended Dosage of VOQUEZNA TRIPLE PAK and VOQUEZNA DUAL PAK in Patients with Hepatic Impairment
Classification | Recommended Dosage
Classification | VOQUEZNA TRIPLE PAK | VOQUEZNA DUAL PAK
Child-Pugh Class A | 20 mg vonoprazan twice daily 1,000 mg amoxicillin twice daily 500 mg clarithromycin twice daily | 20 mg vonoprazan twice daily 1,000 mg amoxicillin three times daily
Child-Pugh Class B | Use is not recommended
Child-Pugh Class C | Use is not recommended

2.5 Missed Doses

If a dose is missed, administer VOQUEZNA TRIPLE PAK or VOQUEZNA DUAL PAK as soon as possible, within 4 hours after the missed dose. If more than 4 hours have passed, skip the missed dose and administer the next dose on the regularly scheduled time. Patients should continue the normal dosing schedule until the medication is completed.

3 DOSAGE FORMS AND STRENGTHS

3.1 VOQUEZNA TRIPLE PAK

VOQUEZNA TRIPLE PAK is a co-package consisting of 14 administration packs for morning and evening dosing. Each administration pack contains the following three drug products:

- Vonoprazan Tablets, 20 mg: pale red, oval, film-coated tablets debossed V20 on one side and plain on the other side.
- Amoxicillin Capsules, 500 mg: yellow, opaque, hard gelatin capsules imprinted with AMOX 500 on one side and GG 849 on the other side.
- Clarithromycin Tablets, 500 mg: white, oval, film-coated debossed GG C9 on one side and plain on the other side.

3.2 VOQUEZNA DUAL PAK

VOQUEZNA DUAL PAK is a co-package consisting of 14 administration packs for morning, mid-day, and evening dosing. Each administration pack contains the following two drug products:

- Vonoprazan Tablets, 20 mg: pale red, oval, film-coated tablets debossed V20 on one side and plain on the other side.
- Amoxicillin Capsules, 500 mg: yellow, opaque, hard gelatin capsules imprinted with AMOX 500 on one side and GG 849 on the other side.

4 CONTRAINDICATIONS

4.1 Contraindications to VOQUEZNA TRIPLE PAK and VOQUEZNA DUAL PAK

Hypersensitivity Reactions

VOQUEZNA TRIPLE PAK and VOQUEZNA DUAL PAK are contraindicated in patients with a known hypersensitivity to any component of VOQUEZNA TRIPLE PAK: vonoprazan, amoxicillin (or other β-lactam antibacterials, e.g., penicillins and cephalosporins), or clarithromycin (or other macrolide antibacterial drugs, e.g., erythromycin) or VOQUEZNA DUAL PAK: vonoprazan or amoxicillin (or other β-lactam antibacterials, e.g., penicillins and cephalosporins) [see Warnings and Precautions (5.1)].

Rilpivirine-containing Products

VOQUEZNA TRIPLE PAK and VOQUEZNA DUAL PAK are contraindicated with rilpivirine-containing products [see Drug Interactions (7)].

4.2 Additional Contraindications to VOQUEZNA TRIPLE PAK Due to the Clarithromycin Component

Serious Adverse Reactions/Risks Due to Drug Interactions

Because of the clarithromycin component, VOQUEZNA TRIPLE PAK is contraindicated with concomitant use of:

- Pimozide: There have been postmarketing reports of drug interactions when clarithromycin is co-administered with pimozide, resulting in cardiac arrhythmias (QT prolongation, ventricular tachycardia, ventricular fibrillation, and torsades de pointes) most likely due to inhibition of metabolism of these drugs by clarithromycin. Fatalities have been reported [see Warnings and Precautions (5.2) and Drug Interactions (7)].
- Lipid-lowering Agents: Lomitapide, simvastatin, and lovastatin [see Warnings and Precautions (5.2) and Drug Interactions (7)]
- Ergot Alkaloids: Ergotamine or dihydroergotamine [see Drug Interactions (7)]
- Colchicine in patients with renal or hepatic impairment [see Warnings and Precautions (5.2) and Drug Interactions (7)]
- Lurasidone: Coadministration of clarithromycin and lurasidone may lead to an increase in lurasidone exposure and the potential for serious adverse reactions [see Drug Interactions (7)].

Cholestatic Jaundice/Hepatic Dysfunction

VOQUEZNA TRIPLE PAK is contraindicated in patients with a history of cholestatic jaundice or hepatic dysfunction associated with prior use of clarithromycin.

5 WARNINGS AND PRECAUTIONS

5.1 Warnings and Precautions for VOQUEZNA TRIPLE PAK and VOQUEZNA DUAL PAK

Hypersensitivity Reactions

Serious and occasionally fatal hypersensitivity reactions (e.g., anaphylaxis, anaphylactic shock, rash, erythema multiforme, and Henoch-Schonlein purpura) have been reported with components of VOQUEZNA TRIPLE PAK and VOQUEZNA DUAL PAK [see Contraindications (4.1)].

Before initiating therapy with VOQUEZNA TRIPLE PAK or VOQUEZNA DUAL PAK careful inquiry should be made regarding previous hypersensitivity reactions to penicillins, cephalosporins, macrolide antibacterial drugs or other allergens. Discontinue VOQUEZNA TRIPLE PAK or VOQUEZNA DUAL PAK immediately and institute appropriate treatment if hypersensitivity occurs.

Acute Tubulointerstitial Nephritis

Acute tubulointerstitial nephritis (TIN) has been reported with vonoprazan, a component of VOQUEZNA TRIPLE PAK or VOQUEZNA DUAL PAK [see Adverse Reactions (6.1)]. If suspected, discontinue VOQUEZNA TRIPLE PAK or VOQUEZNA DUAL PAK and evaluate patients with suspected acute TIN.

Severe Cutaneous Adverse Reactions

Severe cutaneous adverse reactions (SCAR), including Stevens-Johnson syndrome (SJS) and toxic epidermal necrolysis (TEN) have been reported with the components of VOQUEZNA TRIPLE PAK: vonoprazan, amoxicillin, and clarithromycin and VOQUEZNA DUAL PAK: vonoprazan and amoxicillin [see Adverse Reactions (6.2)]. In addition, drug reaction with eosinophilia and systemic symptoms (DRESS), and acute generalized exanthematous pustulosis (AGEP) have been reported with amoxicillin and clarithromycin.

Discontinue VOQUEZNA TRIPLE PAK or VOQUEZNA DUAL PAK at the first signs or symptoms of SCAR or other signs of hypersensitivity and consider further evaluation.

Drug-Induced Enterocolitis Syndrome

Drug-induced enterocolitis syndrome (DIES) has been reported with use of amoxicillin, a component of VOQUEZNA TRIPLE PAK and VOQUEZNA DUAL PAK [see Adverse Reactions (6.2)], with most cases occurring in pediatric patients ≤18 years of age. DIES is a non-IgE mediated hypersensitivity reaction characterized by protracted vomiting occurring 1 to 4 hours after drug ingestion in the absence of skin or respiratory symptoms. DIES may be associated with pallor, lethargy, hypotension, shock, diarrhea within 24 hours after ingesting amoxicillin, and leukocytosis with neutrophilia. If DIES occurs, discontinue VOQUEZNA TRIPLE PAK or VOQUEZNA DUAL PAK and institute appropriate therapy.

Clostridioides difficile-Associated Diarrhea

Clostridioides difficile-associated diarrhea (CDAD) has been reported with use of acid suppressing therapies and nearly all antibacterial agents, including amoxicillin (component of VOQUEZNA DUAL PAK and TRIPLE PAK) and clarithromycin (component of VOQUEZNA TRIPLE PAK), and may range in severity from mild diarrhea to fatal colitis. Treatment with antibacterial agents alters the normal flora of the colon leading to overgrowth of Clostridioides difficile (C. difficile).

C. difficile produces toxins A and B which contribute to the development of CDAD. Hypertoxin-producing strains of C. difficile cause increased morbidity and mortality, as these infections can be refractory to antimicrobial therapy and may require colectomy. CDAD must be considered in all patients who present with diarrhea following antibacterial use. Careful medical history is necessary since CDAD has been reported to occur over two months after the administration of antibacterial agents.

If CDAD is confirmed, VOQUEZNA TRIPLE PAK and VOQUEZNA DUAL PAK should be discontinued. Appropriate fluid and electrolyte management, protein supplementation, antibacterial treatment of C. difficile, and surgical evaluation should be instituted as clinically indicated.

Rash in Patients with Mononucleosis

A high percentage of patients with mononucleosis who receive amoxicillin (a component of VOQUEZNA TRIPLE PAK and VOQUEZNA DUAL PAK) develop an erythematous skin rash. Avoid use of VOQUEZNA TRIPLE PAK and VOQUEZNA DUAL PAK in patients with mononucleosis.

Interactions with Diagnostic Investigations for Neuroendocrine Tumors

Serum chromogranin A (CgA) levels increase secondary to drug-induced decreases in gastric acidity. The increased CgA level may cause false positive results in diagnostic investigations for neuroendocrine tumors. Assess CgA levels at least 4 weeks after VOQUEZNA TRIPLE PAK and VOQUEZNA DUAL PAK treatment and consider repeating the test if initial CgA levels are high [see Drug Interactions (7) and Clinical Pharmacology (12.2)].

Development of Drug-Resistant Bacteria

Prescribing VOQUEZNA TRIPLE PAK or VOQUEZNA DUAL PAK in the absence of a proven or strongly suspected bacterial infection or prophylactic indication is unlikely to provide benefit to the patient, and increases the risk of the development of drug-resistant bacteria.

5.2 Additional Warnings and Precautions for VOQUEZNA TRIPLE PAK Due to the Clarithromycin Component

QT Prolongation

Clarithromycin (a component of VOQUEZNA TRIPLE PAK) has been associated with prolongation of the QT interval and infrequent cases of arrhythmia. Cases of torsades de pointes have been spontaneously reported during postmarketing surveillance in patients receiving clarithromycin. Fatalities have been reported.

Avoid VOQUEZNA TRIPLE PAK in the following patients:

- Patients with known prolongation of QT interval, ventricular cardiac arrhythmia, including torsades de pointes.
- Patients receiving drugs known to prolong the QT interval (e.g., pimozide).
- Patients with ongoing proarrhythmic conditions such as uncorrected hypokalemia or hypomagnesemia, clinically significant bradycardia and in patients receiving Class IA (e.g., quinidine, procainamide, disopyramide) or Class III (dofetilide, amiodarone, sotalol) antiarrhythmic agents.

Elderly patients may be more susceptible to drug-associated effects on the QT interval [see Use in Specific Populations (8.5)].

Hepatotoxicity

Hepatic dysfunction, including increased liver enzymes, and hepatocellular and/or cholestatic hepatitis, with or without jaundice, has been reported with clarithromycin (a component of VOQUEZNA TRIPLE PAK). This hepatic dysfunction may be severe and is usually reversible. In some instances, hepatic failure with fatal outcome has been reported and generally has been associated with serious underlying diseases and/or concomitant medications. Symptoms of hepatitis can include anorexia, jaundice, dark urine, pruritus, or tender abdomen.

Discontinue VOQUEZNA TRIPLE PAK immediately if signs and symptoms of hepatitis occur.

Serious Adverse Reactions Due to Concomitant Use of Clarithromycin with Other Drugs

Drugs metabolized by CYP3A4

Serious adverse reactions have been reported in patients taking clarithromycin (a component of VOQUEZNA TRIPLE PAK) concomitantly with CYP3A4 substrates. These include colchicine toxicity with colchicine; markedly increased transaminases with lomitapide; rhabdomyolysis with simvastatin, lovastatin, and atorvastatin; hypoglycemia and cardiac arrhythmias (e.g., torsades de pointes) with disopyramide; and hypotension and acute kidney injury with calcium channel blockers metabolized by CYP3A4 (e.g., verapamil, amlodipine, diltiazem, nifedipine). Most reports of acute kidney injury with calcium channel blockers metabolized by CYP3A4 involved elderly patients 65 years of age or older [see Contraindications (4.2) and Drug Interactions (7)].

Colchicine

Life-threatening and fatal drug interactions have been reported in patients treated with clarithromycin (a component of VOQUEZNA TRIPLE PAK) and colchicine. If co-administration of VOQUEZNA TRIPLE PAK and colchicine is necessary in patients with normal renal and hepatic function, reduce the dose of colchicine. Monitor patients for clinical symptoms of colchicine toxicity. Concomitant administration of VOQUEZNA TRIPLE PAK and colchicine is contraindicated in patients with renal or hepatic impairment [see Contraindications (4.2) and Drug Interactions (7)].

Lomitapide

Concomitant use of VOQUEZNA TRIPLE PAK with lomitapide may increase the risk of elevation in transaminases due to the clarithromycin component. Concomitant use of VOQUEZNA TRIPLE PAK with lomitapide is contraindicated [see Contraindications (4.2) and Drug Interactions (7)]. If treatment with VOQUEZNA TRIPLE PAK cannot be avoided, therapy with lomitapide must be suspended during the course of treatment.

HMG-CoA Reductase Inhibitors (statins)

Concomitant use of VOQUEZNA TRIPLE PAK with lovastatin or simvastatin may increase these drug's plasma concentrations due to the clarithromycin component, which may increase the risk of myopathy, including rhabdomyolysis. Cases of rhabdomyolysis have been reported in patients treated concomitantly with clarithromycin (a component of VOQUEZNA TRIPLE PAK) and lovastatin or simvastatin. Concomitant use of VOQUEZNA TRIPLE PAK with lovastatin or simvastatin is contraindicated [see Contraindications (4.2)]. If treatment with VOQUEZNA TRIPLE PAK cannot be avoided, therapy with lovastatin or simvastatin must be suspended during the course of treatment. Exercise caution when prescribing VOQUEZNA TRIPLE PAK with atorvastatin or pravastatin [see Drug Interactions (7)].

Hypoglycemic Agents/Insulin

Concomitant use of VOQUEZNA TRIPLE PAK, and hypoglycemic agents (such as nateglinide, pioglitazone, repaglinide, or rosiglitazone) and/or insulin can result in significant hypoglycemia due to the clarithromycin component. Carefully monitor glucose levels when these drugs are used concomitantly with VOQUEZNA TRIPLE PAK [see Drug Interactions (7)].

Quetiapine

Concomitant use of VOQUEZNA TRIPLE PAK with quetiapine could result in somnolence, orthostatic hypotension, altered state of consciousness, neuroleptic malignant syndrome, and QT prolongation due to the clarithromycin component. Refer to quetiapine prescribing information for recommended dosage reduction if co-administered with VOQUEZNA TRIPLE PAK [see Drug Interactions (7)].

Warfarin

There is a risk of serious hemorrhage and significant elevations in the international normalized ratio (INR) and prothrombin time when clarithromycin (a component of VOQUEZNA TRIPLE PAK) is used concomitantly with warfarin. Monitor INR and prothrombin times frequently when warfarin is used concomitantly with VOQUEZNA TRIPLE PAK.

Benzodiazepines

Increased sedation and prolongation of sedation have been reported with concomitant administration when clarithromycin (a component of VOQUEZNA TRIPLE PAK), and triazolobenzodiazepines, such as triazolam and midazolam. Closely monitor patients for signs or symptoms of increased or prolonged central nervous system effects when benzodiazepines such astriazolam or midazolam are used concomitantly with VOQUEZNA TRIPLE PAK [see Drug Interactions (7)].

Embryo-Fetal Toxicity with Use of VOQUEZNA TRIPLE PAK

Based on findings from animal studies and human observational studies in pregnant women with use of clarithromycin, VOQUEZNA TRIPLE PAK is not recommended for use in pregnant women except in clinical circumstances where no alternative therapy is appropriate. If VOQUEZNA TRIPLE PAK is used during pregnancy, or if pregnancy occurs while the patient is taking this drug, advise the patient of the potential risk to the fetus. Clarithromycin demonstrated adverse effects on pregnancy outcome and/or embryo-fetal development, in pregnant animals administered oral clarithromycin. Observational studies in pregnant women also demonstrated adverse effects on pregnancy outcomes, including an increased risk of miscarriage and in some studies an increased incidence of fetal malformations [see Use in Specific Populations (8.1)].

Exacerbation of Myasthenia Gravis

Exacerbation of symptoms of myasthenia gravis and new onset of symptoms of myasthenic syndrome has been reported in patients receiving clarithromycin therapy (a component of VOQUEZNA TRIPLE PAK). Monitor patients for symptoms.

6 ADVERSE REACTIONS

The following serious adverse reactions are described below and elsewhere in labeling:

- Hypersensitivity Reactions [see Warnings and Precautions (5.1)]
- Drug-Induced Enterocolitis Syndrome (DIES) [see Warnings and Precautions (5.1)]
- Acute Tubulointerstitial Nephritis [see Warnings and Precautions (5.1)]
- Clostridioides difficile-Associated Diarrhea [see Warnings and Precautions (5.1)]
- QT Prolongation [see Warnings and Precautions (5.2)]
- Hepatotoxicity [see Warnings and Precautions (5.2)]
- Serious Adverse Reactions Due to Concomitant Use with Other Drugs [see Warnings and Precautions (5.2)]
- Exacerbation of Myasthenia Gravis [see Warnings and Precautions (5.2)]

6.1 Clinical Trials Experience

Because clinical trials are conducted under widely varying conditions, adverse reaction rates observed in the clinical trials of a drug cannot be directly compared to rates in the clinical trials of another drug and may not reflect the rates observed in practice.

Adverse Reactions with VOQUEZNA TRIPLE PAK and VOQUEZNA DUAL PAK

The safety of VOQUEZNA TRIPLE PAK was evaluated in 675 adult patients (aged 20 to 82 years) in clinical trials in the United States, Europe and Japan and VOQUEZNA DUAL PAK was evaluated in 348 adult patients (aged 20 to 80 years) in a clinical trial in the United States and Europe. All the patients were screened and found to be positive for H. pylori infection.

The safety of VOQUEZNA TRIPLE PAK and VOQUEZNA DUAL PAK was evaluated in a randomized, controlled, double-blind triple therapy/open-label dual therapy study conducted in the United States and Europe in treatment-naïve H. pylori-positive adult patients. Patients were randomized 1:1:1 to vonoprazan 20 mg twice daily plus amoxicillin 1,000 mg twice daily plus clarithromycin 500 mg twice daily (VOQUEZNA TRIPLE PAK) or vonoprazan 20 mg twice daily plus amoxicillin 1,000 mg three times daily (VOQUEZNA DUAL PAK) or lansoprazole 30 mg twice daily plus amoxicillin 1,000 mg twice daily plus clarithromycin 500 mg twice daily (LAC) administered for 14 consecutive days. A total of 346 patients received VOQUEZNA TRIPLE PAK in the study, 348 received VOQUEZNA DUAL PAK and 345 received LAC. These patients had a mean age of 51 years (range 20 to 87 years); 62.2% were female, 89.3% were White, 7.4% Black or African American, 1.5% were Asian and 1.8% were others with 72.5% non-Hispanic or Latino.

Adverse Reactions Leading to Discontinuation

Treatment discontinuation due to an adverse reaction occurred in 2.3% (8/346) of the VOQUEZNA TRIPLE PAK-treated patients, 0.9% (3/348) of the VOQUEZNA DUAL PAK-treated patients and 1.2% (4/345) of the LAC-treated patients. The most common adverse reactions leading to discontinuation of VOQUEZNA TRIPLE PAK were diarrhea (0.6%) and hypertension (0.6%) and the most common adverse reaction leading to discontinuation of VOQUEZNA DUAL PAK was rash (0.6%).

Most Common Adverse Reactions

The adverse reactions occurring in ≥2% of patients are described in Table 3.

Table 3: Adverse Reactions Occurring in ≥2% of Adult Patients Receiving VOQUEZNA DUAL PAK or VOQUEZNA TRIPLE PAK
Adverse Reactions | VOQUEZNA DUAL PAK | VOQUEZNA TRIPLE PAK | LAC
 | (N=348) n (%) | (N=346) n (%) | (N=345) n (%)
Diarrhea | 18 (5.2) | 14 (4.0) | 33 (9.6)
Dysgeusia [Dysgeusia also includes taste disorder.] | 2 (0.6) | 16 (4.6) | 21 (6.1)
Vulvovaginal candidiasis [Vulvovaginal candidiasis includes: urogenital infection fungal, vulvovaginal candidiasis, vulvovaginal mycotic infection, vulvovaginal pruritus, pruritus genital, genital infection fungal.] | 7 (2.0) | 11 (3.2) | 5 (1.4)
Abdominal pain [Abdominal pain includes: abdominal discomfort, abdominal pain, abdominal pain lower, abdominal pain upper.] | 9 (2.6) | 8 (2.3) | 10 (2.9)
Headache | 5 (1.4) | 9 (2.6) | 5 (1.4)
Hypertension [Hypertension also includes blood pressure increased.] | 4 (1.1) | 7 (2.0) | 3 (0.9)
Nasopharyngitis | 7 (2.0) | 1 (0.3) | 3 (0.9)

This study was not designed to evaluate meaningful comparisons of the incidence of adverse reactions in the VOQUEZNA DUAL PAK, VOQUEZNA TRIPLE PAK, and LAC treatment groups.

Other Adverse Reactions

Other adverse reactions occurring in <2% of patients with VOQUEZNA TRIPLE PAK or VOQUEZNA DUAL PAK are listed below by body system:

Blood and lymphatic system disorders: anemia, leukocytosis, leukopenia, neutropenia.

Cardiac disorders: QT prolongation, tachycardia.

Eye disorders: orbital edema.

Gastrointestinal disorders: abdominal distension, constipation, dry mouth, duodenal polyp, duodenal ulcer, dyspepsia, flatulence, gastric ulcer, gastroesophageal reflux disease, hematochezia, large intestine polyp, nausea, rectal polyp, stomatitis, tongue discomfort, vomiting.

General disorders and administration site conditions: fatigue, pyrexia.

Immune system disorders: drug hypersensitivity.

Infections and infestations: anal fungal infection, gastrointestinal viral infection, oral fungal infection, pneumonia, tongue fungal infection, upper respiratory tract infection, urinary tract infection, viral infection.

Investigations: increased liver function test.

Metabolism and nutrition disorders: decreased appetite.

Musculoskeletal system: bone fracture.

Nervous system disorders: ageusia, dizziness, tension headache.

Psychiatric disorders: anxiety, depression, insomnia.

Renal and urinary disorders: renal hypertrophy, tubulointerstitial nephritis.

Reproductive system and breast disorders: vaginal discharge.

Respiratory, thoracic and mediastinal disorders: cough, nasal polyps, oropharyngeal pain.

Skin and subcutaneous tissue disorders: dermatitis, dry skin, rash.

6.2 Postmarketing Experience with Components of VOQUEZNA TRIPLE PAK and VOQUEZNA DUAL PAK

The following adverse reactions have been identified during post-approval use of vonoprazan (outside of the United States), amoxicillin, or clarithromycin (all used separately). Because these reactions are reported voluntarily from a population of uncertain size, it is not always possible to reliably estimate their frequency or establish a causal relationship to drug exposure.

Vonoprazan

Blood and lymphatic system disorders: thrombocytopenia.

Immune system disorders: anaphylactic shock, urticaria [see Contraindications (4.1)].

Infections and Infestations: C. difficile (with concomitant antibacterials).

Investigation: hypomagnesemia, hypokalemia, hypocalcemia, vitamin B12 deficiency.

Hepatobiliary disorders: hepatic injury, hepatic failure, jaundice.

Skin and subcutaneous tissue disorders: drug eruption, erythema multiforme, SJS, TEN.

Amoxicillin

Infections and infestations: mucocutaneous candidiasis.

Gastrointestinal: Drug-induced enterocolitis syndrome (DIES), black hairy tongue, and hemorrhagic/pseudomembranous colitis. Onset of pseudomembranous colitis symptoms may occur during or after antibacterial treatment.

Hypersensitivity reactions: anaphylaxis [see Contraindications (4.1)]. Serum sickness–like reactions, erythematous maculopapular rashes, erythema multiforme, exfoliative dermatitis, hypersensitivity vasculitis, and urticaria have been reported.

Renal: crystalluria has been reported [see Overdosage (10)].

Hemic and lymphatic systems: hemolytic anemia, thrombocytopenia, thrombocytopenic purpura, eosinophilia, and agranulocytosis have been reported during therapy with penicillins. These reactions are usually reversible on discontinuation of therapy and are believed to be hypersensitivity phenomena.

Central nervous system: reversible hyperactivity, agitation, confusion, convulsions, aseptic meningitis, and behavioral changes have been rarely reported.

Miscellaneous: tooth discoloration (brown, yellow, or gray staining) has been reported. Most reports occurred in pediatric patients. Discoloration was reduced or eliminated with brushing or dental cleaning in most cases.

Skin and subcutaneous tissue disorders: TEN, SJS, DRESS, AGEP, and linear IgA bullous dermatosis.

Clarithromycin

Blood and lymphatic system: thrombocytopenia, agranulocytosis.

Cardiac: ventricular arrhythmia, torsades de pointes.

Ear and labyrinth: deafness was reported chiefly in elderly women and was usually reversible.

Gastrointestinal: pancreatitis acute, tongue discoloration, tooth discoloration was reported and was usually reversible with professional cleaning upon discontinuation of the drug.

Hepatobiliary: hepatic failure, jaundice hepatocellular. Adverse reactions related to hepatic dysfunction have been reported with clarithromycin.

Infections and infestations: pseudomembranous colitis.

Immune system: anaphylactic reactions, angioedema.

Investigations: prothrombin time prolonged, white blood cell count decreased, INR increased. Abnormal urine color has been reported, associated with hepatic failure.

Metabolism and nutrition: hypoglycemia has been reported in patients taking oral hypoglycemic agents or insulin.

Musculoskeletal and connective tissue: myopathy rhabdomyolysis was reported and in some of the reports, clarithromycin was administered concomitantly with statins, fibrates, colchicine or allopurinol [see Contraindications (4.2)].

Nervous system: parosmia, anosmia, paresthesia and convulsions.

Psychiatric: abnormal behavior, confusional state, depersonalization, disorientation, hallucination, manic behavior, abnormal dream, psychotic disorder. These disorders usually resolve upon discontinuation of the drug.

Renal and urinary: renal failure.

Skin and subcutaneous tissue disorders: TEN, SJS, DRESS, AGEP, Henoch-Schonlein purpura, acne.

Vascular: hemorrhage.

7 DRUG INTERACTIONS

Collated drug interaction information for the individual components in VOQUEZNA TRIPLE PAK and VOQUEZNA DUAL PAK is summarized below. Drug interaction studies with VOQUEZNA TRIPLE PAK or VOQUEZNA DUAL PAK have not been conducted.

These recommendations are based on either drug interaction trials or predicted interactions due to the expected magnitude of interaction and potential for serious adverse reactions or loss of efficacy [see Clinical Pharmacology (12.3)].

Clarithromycin (a component of VOQUEZNA TRIPLE PAK) is a strong CYP3A inhibitor. Concomitant use of VOQUEZNA TRIPLE PAK with a drug(s) primarily metabolized by CYP3A may cause elevations in CYP3A substrate drug's concentrations that could increase or prolong both therapeutic and adverse effects of the concomitant drug.

Table 4: Effects of Other Drugs on VOQUEZNA TRIPLE PAK
Strong or Moderate CYP3A Inducers
Clinical Effect | Vonoprazan and clarithromycin are CYP3A substrates. Strong or moderate CYP3A inducers may decrease exposure of vonoprazan and clarithromycin [see Clinical Pharmacology (12.3)], which may reduce the effectiveness of VOQUEZNA TRIPLE PAK.
Prevention or Management | Avoid concomitant use with VOQUEZNA TRIPLE PAK.
Probenecid
Clinical Effect | Amoxicillin undergoes tubular secretion. Probenecid may increase amoxicillin exposure by blocking its renal tubular secretion, which may increase the risk of VOQUEZNA TRIPLE PAK adverse reactions.
Prevention or Management | Closely monitor for signs or symptoms of increased or prolonged adverse reactions associated with amoxicillin when used with VOQUEZNA TRIPLE PAK.
Allopurinol
Clinical Effect | Increase in the incidence of rashes is reported in patients receiving both allopurinol and amoxicillin together compared to patients receiving amoxicillin alone. It is not known whether this potentiation of amoxicillin rashes is due to allopurinol or the hyperuricemia present in these patients.
Prevention or Management | Discontinue allopurinol at the first appearance of skin rash when used concomitantly with VOQUEZNA TRIPLE PAK.
Omeprazole
Clinical Effect | Clarithromycin concentrations in the gastric tissue and mucus were increased by concomitant administration of omeprazole [see Clinical Pharmacology (12.3)].
Prevention or Management | Avoid concomitant use of VOQUEZNA TRIPLE PAK with omeprazole.
Itraconazole
Clinical Effect | Both clarithromycin and itraconazole are substrates and inhibitors of CYP3A, potentially leading to a bi-directional drug interaction when administered concomitantly. VOQUEZNA TRIPLE PAK's use with strong CYP3A4 inhibitors may lead to increases in clarithromycin exposure, which may increase the risk of VOQUEZNA TRIPLE PAK adverse reactions.
Prevention or Management | Patients taking itraconazole with VOQUEZNA TRIPLE PAK should be monitored closely for signs or symptoms of increased or prolonged adverse reactions associated with itraconazole and clarithromycin.
Antivirals
Clinical Effect | Clarithromycin is a CYP3A4 substrate and inhibitor. Use of VOQUEZNA TRIPLE PAK with antivirals that are CYP3A substrates, inducers, or CYP3A inhibitors may potentially lead to bi-directional drug interactions leading to alterations in exposure of clarithromycin and/or CYP3A substrates, which may increase the risk of adverse reactions or loss of effectiveness [see Clinical Pharmacology (12.3)].
Prevention or Management | Saquinavir (CYP3A substrate and inhibitor) | Use VOQUEZNA TRIPLE PAK with caution. See saquinavir prescribing information for instructions when saquinavir (with or without ritonavir) is co-administered with clarithromycin.
 | Ritonavir (CYP3A inhibitor) | Use of VOQUEZNA TRIPLE PAK with ritonavir is not recommended in patients with decreased renal function.
 | Etravirine (CYP3A inducer) | Avoid concomitant use with VOQUEZNA TRIPLE PAK.

Table 5: Effects of Other Drugs on VOQUEZNA DUAL PAK
Strong or Moderate CYP3A Inducers
Clinical Effect | Vonoprazan is a CYP3A substrate. Strong or moderate CYP3A inducers may decrease vonoprazan exposure [see Clinical Pharmacology (12.3)], which may reduce the effectiveness of VOQUEZNA DUAL PAK.
Prevention or Management | Avoid concomitant use with VOQUEZNA DUAL PAK.
Probenecid
Clinical Effect | Amoxicillin undergoes tubular secretion. Probenecid may increase amoxicillin exposure by blocking its renal tubular secretion, which may increase the risk of VOQUEZNA DUAL PAK adverse reactions.
Prevention or Management | Closely monitor for signs or symptoms of increased or prolonged adverse reactions associated with amoxicillin when used with VOQUEZNA DUAL PAK.
Allopurinol
Clinical Effect | Increase in the incidence of rashes is reported in patients receiving both allopurinol and amoxicillin together compared to patients receiving amoxicillin alone. It is not known whether this potentiation of amoxicillin rashes is due to allopurinol or the hyperuricemia present in these patients.
Prevention or Management | Discontinue allopurinol at the first appearance of skin rash when used concomitantly with VOQUEZNA DUAL PAK.

Table 6: Effects of VOQUEZNA TRIPLE PAK on Other Drugs
Drugs Dependent on Gastric pH for Absorption
Antiretrovirals
Clinical Effect | Vonoprazan reduces intragastric acidity [see Clinical Pharmacology (12.2)], which may alter the absorption of antiretroviral drugs leading to changes in their safety and/or effectiveness.
Prevention or Management | Rilpivirine-containing Products | Concomitant use with VOQUEZNA TRIPLE PAK is contraindicated.
Prevention or Management | Atazanavir | Avoid concomitant use with VOQUEZNA TRIPLE PAK.
Prevention or Management | Nelfinavir | Avoid concomitant use with VOQUEZNA TRIPLE PAK.
Prevention or Management | Other Antiretroviral Drugs | See the prescribing information of other antiretroviral drugs dependent on gastric pH for absorption prior to concomitant use with VOQUEZNA TRIPLE PAK.
Other Drugs (e.g., iron salts, erlotinib, dasatinib, nilotinib, mycophenolate mofetil, ketoconazole/itraconazole)
Clinical Effect | Vonoprazan reduces intragastric acidity [see Clinical Pharmacology (12.2)], which may decrease the absorption of drugs reducing their effectiveness.
Prevention or Management | See the prescribing information for other drugs dependent on gastric pH for absorption.
Certain CYP3A Substrates where minimal concentration changes may lead to serious toxicities
Clinical Effect | Clarithromycin is a strong CYP3A inhibitor. Vonoprazan is a weak CYP3A inhibitor [see Clinical Pharmacology (12.3)]. Clarithromycin and vonoprazan may increase exposure of CYP3A4 substrates, which may increase the risk of adverse reactions related to these substrates. There have been spontaneous or published reports of CYP3A based interactions of clarithromycin with tacrolimus and cyclosporine.
Prevention or Management | Immunosuppressants: Tacrolimus, cyclosporine | Frequent monitoring for concentrations and/or adverse reactions related to the substrate drugs when used with VOQUEZNA TRIPLE PAK. Dosage reduction of substrate drugs may be needed. See prescribing information for the relevant substrate drugs.
CYP2C19 Substrates (e.g., clopidogrel, citalopram, cilostazol)
Clinical Effect | Vonoprazan is a CYP2C19 inhibitor [see Clinical Pharmacology (12.3)]. Vonoprazan may reduce plasma concentrations of the active metabolite of clopidogrel and may cause reduction in platelet inhibition. Vonoprazan may increase exposure of CYP2C19 substrate drugs (e.g., citalopram, cilostazol).
Prevention or Management | Clopidogrel | Carefully monitor the efficacy of clopidogrel and consider alternative anti-platelet therapy.
Prevention or Management | Citalopram and Cilostazol | Carefully monitor patients for adverse reactions associated with citalopram and cilostazol. See the prescribing information for dosage adjustments.
Oral Anticoagulants
Clinical Effect | Abnormal prolongation of prothrombin time (increased INR) has been reported in patients receiving amoxicillin and oral anticoagulants.
Prevention or Management | Appropriate monitoring should be undertaken when anticoagulants are prescribed concurrently. Adjustments in the dose of oral anticoagulants may be necessary to maintain the desired level of anticoagulation.
Chromogranin A (CgA) Test for Neuroendocrine Tumors
Clinical Effect | Vonoprazan reduces intragastric acidity [see Clinical Pharmacology (12.2)], which increases chromogranin A (CgA) levels and may cause false positive results in diagnostic investigations for neuroendocrine tumors.
Prevention or Management | Assess CgA levels at least 4 weeks after VOQUEZNA TRIPLE PAK treatment and repeat the test if initial CgA levels are high. If serial tests are performed (e.g., for monitoring), use the same commercial laboratory for testing, as reference ranges between tests may vary.
Interaction with Secretin Stimulation Test
Clinical Effect | Hyper-response in gastrin secretion in response to secretin stimulation test, falsely suggesting gastrinoma.
Prevention or Management | Test should be performed at least 4 weeks after stopping VOQUEZNA TRIPLE PAK to allow gastrin levels to return to normal [see Clinical Pharmacology (12.2)].
Glucose Tests
Clinical Effect | Amoxicillin is primarily excreted in the urine [see Clinical Pharmacology (12.3)]. High urine concentrations of ampicillin or amoxicillin may cause false-positive results when using glucose tests based on the Benedict's copper reduction reaction that determines the amount of reducing substances like glucose in the urine.
Prevention or Management | Use a test based on enzymatic glucose oxidase reactions when testing for glucose in the urine of patients treated with VOQUEZNA TRIPLE PAK.
Itraconazole
Clinical Effect | Both clarithromycin and itraconazole are substrates and inhibitors of CYP3A, potentially leading to a bi-directional drug interaction when administered concomitantly. VOQUEZNA TRIPLE PAK's use with strong CYP3A4 inhibitors may lead to increases in clarithromycin exposure, which may increase the risk of VOQUEZNA TRIPLE PAK adverse reactions.
Prevention or Management | Patients taking itraconazole with VOQUEZNA TRIPLE PAK should be monitored closely for signs or symptoms of increased or prolonged adverse reactions associated with itraconazole and clarithromycin.
Antiarrhythmics
Clinical Effect | Clarithromycin is a strong CYP3A inhibitor. Clarithromycin may increase exposure of antiarrhythmic drugs that are CYP3A substrates, which may increase the risk of adverse reactions related to these substrates including cardiac arrhythmias (e.g., torsades de pointes). There have been spontaneous or published reports of CYP3A based interactions of clarithromycin with disopyramide and quinidine. There have been postmarketing reports of hypoglycemia with the concomitant administration of clarithromycin and disopyramide.
Prevention or Management | Disopyramide | Avoid concomitant use with VOQUEZNA TRIPLE PAK. If concomitant use is unavoidable, monitor patients for QTc prolongation and changes in blood glucose levels.
Prevention or Management | Amiodarone | Avoid concomitant use with VOQUEZNA TRIPLE PAK. If concomitant use is unavoidable, monitor patients for QTc prolongation.
Prevention or Management | Dofetilide | Avoid concomitant use with VOQUEZNA TRIPLE PAK. If concomitant use is unavoidable, monitor patients for QTc prolongation.
Prevention or Management | Procainamide | Avoid concomitant use with VOQUEZNA TRIPLE PAK. If concomitant use is unavoidable, monitor patients for QTc prolongation.
Prevention or Management | Sotalol | Avoid concomitant use with VOQUEZNA TRIPLE PAK. If concomitant use is unavoidable, monitor patients for QTc prolongation.
Prevention or Management | Quinidine | Avoid concomitant use with VOQUEZNA TRIPLE PAK. If concomitant use is unavoidable, monitor patients for QTc prolongation.
Colchicine
Clinical Effect | Clarithromycin is an inhibitor of CYP3A and the efflux transporter, P-glycoprotein (P-gp). Colchicine is a substrate of CYP3A and P-gp. Clarithromycin increases exposure of colchicine [see Clinical Pharmacology (12.3)], which may increase the risk of adverse reactions related to colchicine.
Prevention or Management | Concomitant use of colchicine with VOQUEZNA TRIPLE PAK is contraindicated in patients with renal or hepatic impairment. If co-administration of VOQUEZNA TRIPLE PAK and colchicine is necessary in patients with normal renal or hepatic function, carefully monitor patients for clinical symptoms of colchicine toxicity and refer to the colchicine prescribing information for recommendations on dosage reduction.
Antipsychotics
Clinical Effect | Clarithromycin is a strong CYP3A inhibitor. Clarithromycin may increase exposure of antipsychotic drugs that are CYP3A substrates, which may increase the risk of adverse reactions related to these substrates including the risk of somnolence, orthostatic hypotension, altered state of consciousness, neuroleptic malignant syndrome, or cardiac arrhythmias (QT prolongation, ventricular tachycardia, ventricular fibrillation, and torsades de pointes).
Prevention or Management | Pimozide | Concomitant use with VOQUEZNA TRIPLE PAK is contraindicated.
Prevention or Management | Lurasidone | Concomitant use with VOQUEZNA TRIPLE PAK is contraindicated.
Prevention or Management | Quetiapine | Refer to quetiapine prescribing information for recommendations on dosage reduction if co-administered with CYP3A4 inhibitors such as clarithromycin.
Tolterodine (patients deficient in CYP2D6 activity)
Clinical Effect | Clarithromycin is a strong CYP3A inhibitor. The primary route of metabolism for tolterodine is via CYP2D6. Clarithromycin may increase tolterodine exposure and the risk of adverse reactions related to tolterodine in patients deficient in CYP2D6 activity because tolterodine is metabolized via CYP3A in this subset of population.
Prevention or Management | Tolterodine 1 mg twice daily is recommended in patients deficient in CYP2D6 activity (poor metabolizers) when co-administered with strong CYP3A4 inhibitors such as clarithromycin.
Antivirals
Clinical Effect | Clarithromycin is a CYP3A4 substrate and inhibitor. Use of VOQUEZNA TRIPLE PAK with antivirals that are CYP3A substrates, inducers, or CYP3A inhibitors may potentially lead to bi-directional drug interactions leading to alterations in exposure of clarithromycin and/or CYP3A substrates, which may increase the risk of adverse reactions or loss of effectiveness [see Clinical Pharmacology (12.3)].
Prevention or Management | Saquinavir (CYP3A substrate and inhibitor) | Use VOQUEZNA TRIPLE PAK with caution. See saquinavir prescribing information for instructions when saquinavir (with or without ritonavir) is co-administered with clarithromycin.
Prevention or Management | Maraviroc (CYP3A substrate) | Use VOQUEZNA TRIPLE PAK with caution. See the prescribing information of maraviroc for dosage recommendation when given with strong CYP3A inhibitors such as clarithromycin.
Prevention or Management | Zidovudine | Administration of VOQUEZNA TRIPLE PAK and zidovudine should be separated by at least two hours.
Benzodiazepines
Clinical Effect | Clarithromycin is a strong CYP3A inhibitor. Clarithromycin may increase exposure of benzodiazepines that are CYP3A substrates, which may increase the risk of adverse reactions related to these substrates [see Warnings and Precautions (5.2) and Clinical Pharmacology (12.3)].
Prevention or Management | Midazolam | Closely monitor patients for signs or symptoms of increased or prolonged central nervous system effects (e.g., somnolence and confusion) and refer to the CYP3A substrate prescribing information for dosage adjustments when used concomitantly with VOQUEZNA TRIPLE PAK.
Prevention or Management | Alprazolam | Closely monitor patients for signs or symptoms of increased or prolonged central nervous system effects (e.g., somnolence and confusion) and refer to the CYP3A substrate prescribing information for dosage adjustments when used concomitantly with VOQUEZNA TRIPLE PAK.
Prevention or Management | Triazolam | Closely monitor patients for signs or symptoms of increased or prolonged central nervous system effects (e.g., somnolence and confusion) and refer to the CYP3A substrate prescribing information for dosage adjustments when used concomitantly with VOQUEZNA TRIPLE PAK.
Calcium Channel Blockers
Clinical Effect | Clarithromycin is a strong CYP3A inhibitor. Clarithromycin may increase exposure of calcium channel blockers that are CYP3A substrates, which may increase the risk of adverse reactions related to these substrates including hypotension, acute kidney injury, bradyarrhythmias, lactic acidosis, or peripheral edema.
Prevention or Management | Verapamil | Use VOQUEZNA TRIPLE PAK with caution.
Prevention or Management | Amlodipine | Use VOQUEZNA TRIPLE PAK with caution.
Prevention or Management | Diltiazem | Use VOQUEZNA TRIPLE PAK with caution.
Prevention or Management | Nifedipine | Use VOQUEZNA TRIPLE PAK with caution.
Ergot Alkaloids
Clinical Effect | Clarithromycin is a strong CYP3A inhibitor. Clarithromycin may increase exposure of ergot alkaloids that are CYP3A substrates, which may increase the risk of vasospasm and ischemia of the extremities and other tissues including the central nervous system [see Contraindications (4.2)].
Prevention or Management | Ergotamine | Concomitant use with VOQUEZNA TRIPLE PAK is contraindicated.
Prevention or Management | Dihydroergotamine | Concomitant use with VOQUEZNA TRIPLE PAK is contraindicated.
Hypoglycemic Agents
Clinical Effect | Clarithromycin is a strong CYP3A inhibitor. Clarithromycin may increase exposure of hypoglycemic agents that are CYP3A substrates, which may increase the risk of hypoglycemia [see Warnings and Precautions (5.2)].
Prevention or Management | Nateglinide | Closely monitor glucose levels when used concomitantly with VOQUEZNA TRIPLE PAK.
Prevention or Management | Pioglitazone | Closely monitor glucose levels when used concomitantly with VOQUEZNA TRIPLE PAK.
Prevention or Management | Repaglinide | Closely monitor glucose levels when used concomitantly with VOQUEZNA TRIPLE PAK.
Prevention or Management | Rosiglitazone | Closely monitor glucose levels when used concomitantly with VOQUEZNA TRIPLE PAK.
Prevention or Management | Insulin | Closely monitor glucose levels when used concomitantly with VOQUEZNA TRIPLE PAK.
Lipid-lowering Agents
Clinical Effect | Clarithromycin is a strong CYP3A inhibitor. Clarithromycin may increase exposure of lipid-lowering drugs that are CYP3A substrates, thereby increasing the risk of toxicities from these drugs [see Warnings and Precautions (5.2)].
Prevention or Management | Lomitapide | Concomitant use with VOQUEZNA TRIPLE PAK is contraindicated.
Prevention or Management | Lovastatin | Concomitant use with VOQUEZNA TRIPLE PAK is contraindicated.
Prevention or Management | Simvastatin | Concomitant use with VOQUEZNA TRIPLE PAK is contraindicated.
Prevention or Management | Atorvastatin | Use VOQUEZNA TRIPLE PAK with caution. In situations where the concomitant use of VOQUEZNA TRIPLE PAK with atorvastatin or pravastatin cannot be avoided, atorvastatin dose should not exceed 20 mg daily and pravastatin dose should not exceed 40 mg daily.
Prevention or Management | Pravastatin | Use VOQUEZNA TRIPLE PAK with caution. In situations where the concomitant use of VOQUEZNA TRIPLE PAK with atorvastatin or pravastatin cannot be avoided, atorvastatin dose should not exceed 20 mg daily and pravastatin dose should not exceed 40 mg daily.
Prevention or Management | Fluvastatin | Use of a statin that is not dependent on CYP3A metabolism (e.g., fluvastatin) can be considered. It is recommended to prescribe the lowest registered dose if concomitant use cannot be avoided.
Phosphodiesterase Inhibitors
Clinical Effect | Clarithromycin is a strong CYP3A inhibitor. Clarithromycin may increase exposure of phosphodiesterase inhibitors that are CYP3A substrates, which may increase the risk of adverse reactions related to these substrates.
Prevention or Management | Sildenafil | Avoid concomitant use with VOQUEZNA TRIPLE PAK. If concomitant use is unavoidable, see the prescribing information of the respective phosphodiesterase inhibitors for dosage recommendation when given with strong CYP3A inhibitors such as clarithromycin.
Prevention or Management | Tadalafil | Avoid concomitant use with VOQUEZNA TRIPLE PAK. If concomitant use is unavoidable, see the prescribing information of the respective phosphodiesterase inhibitors for dosage recommendation when given with strong CYP3A inhibitors such as clarithromycin.
Prevention or Management | Vardenafil | Avoid concomitant use with VOQUEZNA TRIPLE PAK. If concomitant use is unavoidable, see the prescribing information of the respective phosphodiesterase inhibitors for dosage recommendation when given with strong CYP3A inhibitors such as clarithromycin.
Other CYP3A Based Interactions
Clinical Effect | Clarithromycin is a substrate and strong inhibitor of CYP3A4. Clarithromycin increases exposure of CYP3A substrates [see Clinical Pharmacology (12.3)], which may increase the risk of adverse reactions related to these substrates [see Warnings and Precautions (5.2)]. Strong or moderate CYP3A inducers may decrease exposure of clarithromycin. There have been spontaneous or published reports of CYP3A based interactions of clarithromycin with alfentanil, methylprednisolone, cilostazol, bromocriptine, vinblastine, phenobarbital, and St. John's Wort.
Prevention or Management | Use VOQUEZNA TRIPLE PAK with caution.
P-glycoprotein (P-gp) Substrates: Digoxin
Clinical Effect | Clarithromycin is a P-gp inhibitor. Clarithromycin may increase exposure of P-gp substrates, which may increase the risk of adverse reactions related to these substrates, including potentially fatal arrhythmias. Elevated digoxin serum concentrations in patients receiving clarithromycin and digoxin concomitantly have been reported in postmarketing surveillance. Some patients have shown clinical signs consistent with digoxin toxicity, including potentially fatal arrhythmias.
Prevention or Management | Digoxin | Carefully monitor serum concentrations and refer to the digoxin prescribing information for dosage adjustments when used concomitantly with VOQUEZNA TRIPLE PAK.
Drugs Metabolized by CYP450 Isoforms Other than CYP3A
Clinical Effect | Clarithromycin may increase exposure of drugs that are metabolized by CYP450 isoforms other than CYP3A by inhibiting their metabolism. There have been post-marketing reports of interactions of clarithromycin with drugs not thought to be metabolized by CYP3A.
Prevention or Management | Hexobarbital | Use VOQUEZNA TRIPLE PAK with caution.
Prevention or Management | Phenytoin | Use VOQUEZNA TRIPLE PAK with caution.
Prevention or Management | Valproate | Use VOQUEZNA TRIPLE PAK with caution.
Theophylline
Clinical Effect | Clarithromycin may increase exposure of theophylline (a xanthine derivative drug) [see Clinical Pharmacology (12.3)], which may increase the risk of adverse reactions related to theophylline.
Prevention or Management | Closely monitor serum theophylline concentrations in patients receiving high dosages of theophylline or with baseline concentrations in the upper therapeutic range when used concomitantly with VOQUEZNA TRIPLE PAK.

Table 7: Effects of VOQUEZNA DUAL PAK on Other Drugs
Drugs Dependent on Gastric pH for Absorption
Antiretrovirals
Clinical Effect | Vonoprazan reduces intragastric acidity [see Clinical Pharmacology (12.2)], which may alter the absorption of antiretroviral drugs leading to changes in their safety and/or effectiveness.
Prevention or Management | Rilpivirine-containing Products | Concomitant use with VOQUEZNA DUAL PAK is contraindicated.
 | Atazanavir | Avoid concomitant use with VOQUEZNA DUAL PAK.
 | Nelfinavir | Avoid concomitant use with VOQUEZNA DUAL PAK.
 | Other Antiretroviral Drugs | See the prescribing information of other antiretroviral drugs dependent on gastric pH for absorption prior to concomitant use with VOQUEZNA DUAL PAK.
Other Drugs (e.g., iron salts, erlotinib, dasatinib, nilotinib, mycophenolate mofetil, ketoconazole/itraconazole)
Clinical Effect | Vonoprazan reduces intragastric acidity [see Clinical Pharmacology (12.2)], which may decrease the absorption of drugs reducing their effectiveness.
Prevention or Management | See the prescribing information for other drugs dependent on gastric pH for absorption.
Certain CYP3A Substrates where minimal concentration changes may lead to serious toxicities
Clinical Effect | Vonoprazan is a weak CYP3A inhibitor [see Clinical Pharmacology (12.3)]. Vonoprazan may increase exposure of CYP3A4 substrates, which may increase the risk of adverse reactions related to these substrates.
Prevention or Management | Immunosuppressants: Tacrolimus, cyclosporine | Frequent monitoring for concentrations and/or adverse reactions related to the substrate drugs when used with VOQUEZNA DUAL PAK. Dosage reduction of substrate drugs may be needed. See prescribing information for the relevant substrate drugs.
Oral Anticoagulants
Clinical Effect | Abnormal prolongation of prothrombin time (increased INR) has been reported in patients receiving amoxicillin and oral anticoagulants.
Prevention or Management | Appropriate monitoring should be undertaken when anticoagulants are prescribed concurrently. Adjustments in the dose of oral anticoagulants may be necessary to maintain the desired level of anticoagulation.
CYP2C19 Substrates (e.g., clopidogrel, citalopram, cilostazol)
Clinical Effect | Vonoprazan is a CYP2C19 inhibitor [see Clinical Pharmacology (12.3)]. Vonoprazan may reduce plasma concentrations of the active metabolite of clopidogrel and may cause reduction in platelet inhibition. Vonoprazan may increase exposure of CYP2C19 substrate drugs (e.g., citalopram, cilostazol).
Prevention or Management | Clopidogrel | Carefully monitor the efficacy of clopidogrel and consider alternative anti-platelet therapy.
 | Citalopram and Cilostazol | Carefully monitor patients for adverse reactions associated with citalopram and cilostazol. See the prescribing information for dosage adjustments.
CgA Test for Neuroendocrine Tumors
Clinical Effect | Vonoprazan reduces intragastric acidity [see Clinical Pharmacology (12.2)], which increases CgA levels and may cause false positive results in diagnostic investigations for neuroendocrine tumors.
Prevention or Management | Assess CgA levels at least 4 weeks after VOQUEZNA DUAL PAK treatment and repeat the test if initial CgA levels are high. If serial tests are performed (e.g., for monitoring), use the same commercial laboratory for testing, as reference ranges between tests may vary.
Interaction with Secretin Stimulation Test
Clinical Effect | Hyper-response in gastrin secretion in response to secretin stimulation test, falsely suggesting gastrinoma.
Prevention or Management | Test should be performed at least 4 weeks after stopping VOQUEZNA DUAL PAK to allow gastrin levels to return to normal [see Clinical Pharmacology (12.2)].
Glucose Tests
Clinical Effect | Amoxicillin is primarily excreted in the urine [see Clinical Pharmacology (12.3)]. High urine concentrations of ampicillin or amoxicillin may cause false-positive results when using glucose tests based on the Benedict's copper reduction reaction that determines the amount of reducing substances like glucose in the urine.
Prevention or Management | Use a test based on enzymatic glucose oxidase reactions when testing for glucose in the urine of patients treated with VOQUEZNA DUAL PAK.

8 USE IN SPECIFIC POPULATIONS

8.1 Pregnancy

Pregnancy Exposure Registry

There is a pregnancy exposure registry that monitors pregnancy outcomes in women exposed to VOQUEZNA TRIPLE PAK or VOQUEZNA DUAL PAK during pregnancy. Healthcare providers are encouraged to register patients by calling 1-866-609-1612 or visiting https://voqueznapregnancyregistry.com/.

Risk Summary

VOQUEZNA TRIPLE PAK

Based on findings from animal studies and observational studies in pregnant women with use of clarithromycin, use of VOQUEZNA TRIPLE PAK is not recommended in pregnant women except in clinical circumstances where no alternative therapy is appropriate. There are no adequate and well-controlled studies of VOQUEZNA TRIPLE PAK in pregnant women to evaluate for drug-associated risks of major birth defects, miscarriage, or other adverse maternal or fetal outcomes. If VOQUEZNA TRIPLE PAK is used during pregnancy, advise pregnant women of the potential risk to a fetus.

No reproductive and developmental toxicity studies with the combination of vonoprazan, amoxicillin, and/or clarithromycin were conducted.

VOQUEZNA DUAL PAK

There are no adequate and well-controlled studies of VOQUEZNA DUAL PAK in pregnant women to evaluate for drug-associated risks of major birth defects, miscarriage, or other adverse maternal or fetal outcomes.

Individual Components of VOQUEZNA TRIPLE PAK and VOQUEZNA DUAL PAK

Clarithromycin:

Published observational studies in pregnant women have demonstrated adverse effects on pregnancy outcomes, including an increased risk of miscarriage and in some studies an increased incidence of fetal malformations (see Data). In animal reproduction studies, administration of oral clarithromycin to pregnant mice, rats, rabbits, and monkeys during the period of organogenesis produced malformations in rats (cardiovascular anomalies) and mice (cleft palate) at clinically relevant doses. Fetal effects in mice, rats, and monkeys (e.g., reduced fetal survival, body weight, body weight gain) and implantation losses in rabbits were generally considered to be secondary to maternal toxicity (see Data).

Vonoprazan:

Available data from pharmacovigilance reports with vonoprazan use in pregnant women are not sufficient to evaluate for a drug-associated risk for major birth defects, miscarriage or other adverse maternal or fetal outcomes.

In pregnant rats, no adverse effects were noted after oral administration of vonoprazan during organogenesis at approximately 27 times the maximum recommended human dose (MRHD) based on AUC exposure comparisons.

In a pre- and postnatal development (PPND) study, pups from dams orally administered vonoprazan during organogenesis and through lactation, exhibited liver discoloration, which in follow-up mechanistic animal studies was associated with necrosis, fibrosis, and hemorrhage at a dose approximately 22 times the MRHD based on AUC comparisons which were likely attributable to exposure during lactation [see Use in Specific Populations (8.2)]. These effects were not observed at the next lower dose in this study, which was approximately equal to the MRHD based on AUC comparison, however they were seen at clinically relevant exposures in dose range finding studies in rats (see Data).

Amoxicillin:

Available data from published epidemiologic studies and pharmacovigilance case reports over several decades with amoxicillin use have not established drug-associated risks of major birth defects, miscarriage, or adverse maternal or fetal outcomes. Reproduction studies with amoxicillin have been performed in mice and rats (5 and 10 times the human dose 2 g human dose for mice and rats, respectively, 3 and 6 times the 3 g human dose for mice and rats, respectively). There was no evidence of harm to the fetus due to amoxicillin.

The estimated background risks of major birth defects and miscarriage for the indicated population are unknown. All pregnancies have a background risk of birth defect, loss, or other adverse outcomes. In the United States general population, the estimated background risk of major birth defects and miscarriage in clinically recognized pregnancies is 2% to 4% and 15% to 20%, respectively.

Data

Human Data

Clarithromycin:

Available data from prospective and retrospective observational studies with clarithromycin use in pregnant women demonstrate an increased risk of miscarriage. Data from these same studies regarding major congenital malformations are inconsistent, with some studies reporting an increased risk (atrioventricular septal defects, genital malformations, orofacial clefts) and others finding no difference between those exposed to clarithromycin and those exposed to nonteratogenic controls. Available studies have methodologic limitations, including small sample size, under-capture of non-live births, exposure misclassification and inconsistent comparator groups.

Animal Data

Clarithromycin:

Animal reproduction studies were conducted in mice, rats, rabbits, and monkeys with oral and intravenously administered clarithromycin. In pregnant mice, clarithromycin was administered during organogenesis (gestation day [GD] 6 to 15) at oral doses of 15, 60, 250, 500, or 1000 mg/kg/day. Reduced body weight observed in dams at 1000 mg/kg/day (3 times the MRHD based on BSA comparison) resulted in reduced survival and body weight of the fetuses. At ≥ 500 mg/kg/day, increases in the incidence of post-implantation loss and cleft palate in the fetuses were observed. No adverse developmental effects were observed in mice at ≤ 250 mg/kg/day (≤ 1 times MRHD based on BSA comparison).

In pregnant Sprague Dawley rats, clarithromycin was administered during organogenesis (GD 6 to 15) at oral doses of 15, 50, or 150 mg/kg/day. Reductions in body weight and food consumption was observed in dams at 150 mg/kg/day. Increased resorptions and reduced body weight of the fetuses at this dose were considered secondary to maternal toxicity. Additionally, at 150 mg/kg/day (1 times MRHD based on BSA comparison), a low incidence of cardiovascular anomalies (complete situs inversus, undivided truncus, IV septal defect) was observed in the fetuses. Clarithromycin did not cause adverse developmental effects in rats at 50 mg/kg/day (0.3 times MRHD based on BSA comparison). Intravenous dosing of clarithromycin during organogenesis in rats (GD 6 to 15) at 15, 50, or 160 mg/kg/day was associated with maternal toxicity (reduced body weight, body-weight gain, and food consumption) at 160 mg/kg/day but no evidence of adverse developmental effects at any dose (≤ 1 times MRHD based on BSA comparison).

In pregnant Wistar rats, clarithromycin was administered during organogenesis (GD 7 to 17) at oral doses of 10, 40, or 160 mg/kg/day. Reduced body weight and food consumption were observed in dams at 160 mg/kg/day but there was no evidence of adverse developmental effects at any dose (≤ 1 times MRHD based on surface BSA comparison).

In pregnant rabbits, clarithromycin administered during organogenesis (GD 6 to 18) at oral doses of 10, 35, or 125 mg/kg/day resulted in reduced maternal food consumption and decreased body weight at the highest dose, with no evidence of any adverse developmental effects at any dose (≤ 2 times MRHD based on BSA comparison). Intravenously administered clarithromycin to pregnant rabbits during organogenesis (GD 6 to 18) in rabbits at 20, 40, 80, or 160 mg/kg/day (≥ 0.3 times MRHD based on BSA comparison) resulted in maternal toxicity and implantation losses at all doses.

In pregnant monkeys, clarithromycin was administered (GD 20 to 50) at oral doses of 35 or 70 mg/kg/day. Dose-dependent emesis, poor appetite, fecal changes, and reduced body weight were observed in dams at all doses (≥ 0.5 times MRHD based on BSA comparison). Growth retardation in 1 fetus at 70 mg/kg/day was considered secondary to maternal toxicity. There was no evidence of primary drug related adverse developmental effects at any dose tested.

In a reproductive toxicology study in rats administered oral clarithromycin late in gestation through lactation (GD 17 to post-natal day 21) at doses of 10, 40, or 160 mg/kg/day (≤ 1 times MRHD based on BSA comparison), reductions in maternal body weight and food consumption were observed at 160 mg/kg/day. Reduced body-weight gain observed in offspring at 160 mg/kg/day was considered secondary to maternal toxicity. No adverse developmental effects were observed with clarithromycin at any dose tested.

Vonoprazan:

Pregnant rats were orally administered vonoprazan at doses of 30, 100, or 300 mg/kg/day (7, 27, 130 times the MRHD based on AUC comparison at the same doses from unmated female rats from separate studies) during the period of organogenesis from gestation Day 6 to 17. During maternal dosing, one high-dose female died and decreased body weight and food consumption occurred at the middle and highest doses. No embryo-fetal lethality was observed but decreased fetal body weight was observed in the highest dose group. Fetal abnormalities were limited to the 300 mg/kg/day dose group and included ventricular septal defect and mal-positioned subclavian artery in fetuses in a majority (15/19) of litters, as well as tail abnormalities, and small anal opening. No adverse embryo-fetal effects were observed at the 100 mg/kg/day.

Pregnant rabbits were orally administered vonoprazan at doses of 3, 10, or 30 mg/kg/day (0.04, 1.5, 10 times the MRHD based on AUC comparison) during the period of organogenesis from gestation Day 6 to 18. Two animals aborted at the highest dose and decreased body weight and food consumption occurred at the mid and high doses. No embryo-fetal mortality or toxicity occurred. There were no external, visceral or skeletal abnormalities.

In a PPND study, pregnant female rats were orally administered vonoprazan at doses of 1, 3, 10, or 100 mg/kg/day (0.01, 0.18, 1.1, 22 times the MRHD based on AUC comparison) from GD 6 to lactation day (LD) 21. Decreased body weight gain and food consumption were present in dams at the highest dose during lactation. Decreased body weight gain compared to controls was observed in offspring from dams in the high dose group. Liver discoloration occurred in offspring from the high dose group at LD 4 but was not present in animals examined after weaning. Similarly, in dose range finding studies in rats and follow-up mechanistic animal studies, the liver discoloration was observed and characterized as necrosis, fibrosis and hemorrhage at equal to or greater than clinically relevant exposures based on AUC comparisons. The mechanistic studies further demonstrated the effect was likely attributable to vonoprazan exposure during lactation [see Use in Specific Populations (8.2)]. The clinical relevance of the liver findings is uncertain.

Exposure margins from vonoprazan between the animal and clinical studies for vonoprazan, amoxicillin, and clarithromycin used in combination may be lower due to increased vonoprazan exposure from concomitant use with clarithromycin in patients [see Clinical Pharmacology (12.3)].

Amoxicillin:

Available data from published epidemiologic studies and pharmacovigilance case reports over several decades with amoxicillin use have not established drug-associated risks of major birth defects, miscarriage, or other adverse maternal or fetal outcomes. Animal reproduction studies with amoxicillin have been performed in mice and rats, at doses up to 2,000 mg/kg (5 and 10 times the 2 g human dose for mice and rats, respectively, 3 and 6 times the 3 g human dose for mice and rats, respectively, based on BSA comparison). There was no evidence of harm to the fetus due to amoxicillin.

The estimated background risks of major birth defects and miscarriage for the indicated population are unknown. All pregnancies have a background risk of birth defect, loss, or other adverse outcomes. In the United States general population, the estimated background risk of major birth defects and miscarriage in clinically recognized pregnancies is 2% to 4% and 15% to 20%, respectively.

8.2 Lactation

Risk Summary

Vonoprazan:

Data from a clinical lactation study indicate that vonoprazan is present in human breast milk in amounts less than 0.03% of the administered maternal dose. Assuming an infant body weight of 6 kg and an exclusively breastfed infant, the estimated mean daily infant dose was less than 0.3% of the maternal weight-adjusted dose (see Data). There are no data on the effects of vonoprazan on the breastfed child or the effects on milk production. In animal studies, liver injury occurred in offspring from pregnant and lactating rats administered oral vonoprazan at AUC exposures approximately equal to and greater than the MRHD (see Data).

Clarithromycin:

Based on data from a published lactation study, clarithromycin and its active metabolite 14-OH clarithromycin are present in human milk at less than 2% of the maternal weight-adjusted dose (see Data). In a separate observational study of lactating women exposed to clarithromycin, reported adverse effects on breastfed children (rash, diarrhea, loss of appetite, somnolence) were comparable to amoxicillin (see Clinical Considerations). No data are available to assess the effects of clarithromycin or 14-OH clarithromycin on milk production.

Amoxicillin:

Data from published clinical lactation study reports that amoxicillin is present in human milk. There are no data on the effects of amoxicillin on milk production.

Risk and Benefit Statement for VOQUEZNA TRIPLE PAK or VOQUEZNA DUAL PAK:

The developmental and health benefits of breastfeeding should be considered along with the mother’s clinical need for VOQUEZNA TRIPLE PAK or VOQUEZNA DUAL PAK and any potential adverse effects on the breastfed child from VOQUEZNA TRIPLE PAK or VOQUEZNA DUAL PAK or from the underlying maternal condition.

Clinical Considerations

Monitor infants exposed to clarithromycin or amoxicillin through breast milk for diarrhea, vomiting or rash.

Data

Human Data

Vonoprazan:

Concentrations of vonoprazan were measured in breast milk from 15 healthy lactating women following administration of vonoprazan 20 mg once daily (not an approved dosage for VOQUEZNA TRIPLE PAK and VOQUEZNA DUAL PAK) (N=5) or twice daily (N=10) for 4 days (not an approved duration for VOQUEZNA TRIPLE PAK and VOQUEZNA DUAL PAK).
Following administration of a 20 mg vonoprazan twice daily dosage regimen, the mean average concentration (Cavg) of vonoprazan in breast milk at steady state was 13.3 ng/mL. The estimated mean total amount of vonoprazan present in breast milk over 24 hours was 0.009 mg. Assuming an infant body weight of 6 kg and an exclusively breastfed infant, the estimated mean daily infant dose was 0.0015 mg/kg/day, representing 0.27% of the maternal weight-adjusted dose.
Following administration of a 20 mg vonoprazan once daily regimen (not an approved dosage for VOQUEZNA TRIPLE PAK and VOQUEZNA DUAL PAK), the mean average concentration (Cavg) of vonoprazan in breast milk at steady state was 7.55 ng/mL. The estimated mean total amount of vonoprazan present in breast milk over 24 hours was 0.0024 mg. Assuming an infant body weight of 6 kg and an exclusively breastfed infant, the estimated mean daily infant dose was 0.0004 mg/kg/day, representing 0.13% of the maternal weight-adjusted dose.

Clarithromycin:

Serum and milk samples were obtained after 3 days of treatment, at steady state, from one published study of 12 lactating women who were taking clarithromycin 250 mg orally twice daily. Based on data from this study, and assuming milk consumption of 150 mL/kg/day, an exclusively human milk fed infant would receive an estimated average of 136 mcg/kg/day of clarithromycin and its active metabolite, with this maternal dosage regimen. This is less than 2% of the maternal weight-adjusted dose (7.8 mg/kg/day, based on the average maternal weight of 64 kg), and less than 1% of the pediatric dose (15 mg/kg/day) for children greater than 6 months of age.

A prospective observational study of 55 breastfed infants of mothers taking a macrolide antibacterial (6 were exposed to clarithromycin) were compared to 36 breastfed infants of mothers taking amoxicillin. Adverse reactions were comparable in both groups. Adverse reactions occurred in 12.7% of infants exposed to macrolides and included rash, diarrhea, loss of appetite, and somnolence.

Animal Data

No studies with the combination of vonoprazan and amoxicillin, and/or clarithromycin were conducted to examine the effect of lactational exposure on animal offspring.

Vonoprazan:

In a PPND study in rats, in which the dams were administered oral vonoprazan during gestation and through lactation at up to 22-times the MRHD (based on a comparison of AUC), liver discoloration occurred in offspring from the high dose group [see Use in Specific Populations (8.1)].

Liver discoloration associated with necrosis, fibrosis, and hemorrhage in the offspring of dosed rats was also seen in dose-range finding studies and limited, non-standard, follow-up, mechanistic studies, including offspring in lactation only studies. These effects were reported in pups on LD 4 at doses from 3 to 100 mg/kg/day (approximately 0.2- to 22-fold the MRHD based on an AUC values extrapolated from the PPND study) and on LD 14 at doses from 10 to 100 mg/kg/day (approximately 1- to 22-fold the MRHD based on an extrapolated AUC comparisons). In mechanistic studies, liver effects were observed in offspring treated only during lactation but not in offspring from animals only treated during gestation. In some of these studies, this finding was associated with increased offspring stomach weights that was reversed along with liver discoloration by concomitant treatment with a gastrointestinal prokinetic agent.

8.3 Females and Males of Reproductive Potential

Infertility

Males

Clarithromycin:

Based on animal fertility study findings for clarithromycin, VOQUEZNA TRIPLE PAK may impair fertility in males of reproductive potential [see Nonclinical Toxicology (13.1)].

8.4 Pediatric Use

Safety and effectiveness of VOQUEZNA TRIPLE PAK or VOQUEZNA DUAL PAK in pediatric patients have not been established.

8.5 Geriatric Use

Geriatric Use for the Individual Components of VOQUEZNA TRIPLE PAK and VOQUEZNA DUAL PAK

Amoxicillin and Clarithromycin

Amoxicillin and clarithromycin are known to be substantially excreted by the kidney, and the risk of adverse reactions to these drugs may be greater in patients with impaired renal function and it may be useful to monitor renal function [see Use in Specific Populations (8.6)].

Vonoprazan

There were 218 patients aged 65 years and older in the clinical study of VOQUEZNA TRIPLE PAK and VOQUEZNA DUAL PAK for the treatment of H. pylori infection [see Clinical Studies (14)]. Of the total number of vonoprazan-treated subjects (N=694), there were 153 (22.0%) patients aged 65 years and older and 18 (2.6%) patients were aged 75 years and older. No overall differences in safety or effectiveness were observed between these patients and younger adult patients.

Amoxicillin

An analysis of clinical studies of amoxicillin was conducted to determine whether subjects aged 65 and over respond differently from younger subjects. These analyses have not identified differences in responses between the elderly and younger patients, but a greater sensitivity of some older individuals cannot be ruled out.

This drug is known to be substantially excreted by the kidney, and the risk of toxic reactions to this drug may be greater in patients with impaired renal function. Because elderly patients are more likely to have decreased renal function, and it may be useful to monitor renal function.

Clarithromycin

In a steady-state study in which healthy elderly subjects (65 years to 81 years of age) were given 500 mg of clarithromycin every 12 hours, the maximum serum concentrations and area under the curves of clarithromycin and 14-OH clarithromycin were increased compared to those achieved in healthy young adults. These changes in pharmacokinetics parallel known age-related decreases in renal function. In clinical trials, elderly patients did not have an increased incidence of adverse reactions when compared to younger patients. Elderly patients may be more susceptible to development of torsades de pointes arrhythmias than younger patients [see Warnings and Precautions (5.2)].

Most reports of acute kidney injury with calcium channel blockers metabolized by CYP3A4 (e.g., verapamil, amlodipine, diltiazem, nifedipine) involved elderly patients 65 years of age or older [see Warnings and Precautions (5.2)].

Especially in elderly patients, there have been reports of colchicine toxicity with concomitant use of clarithromycin and colchicine, some of which occurred in patients with renal insufficiency. Deaths have been reported in some patients [see Contraindications (4.2) and Warnings and Precautions (5.2)].

8.6 Renal Impairment

No dosage adjustment of VOQUEZNA TRIPLE PAK or VOQUEZNA DUAL PAK is recommended in patients with mild to moderate renal impairment (eGFR 30 to 89 mL/min). Use of VOQUEZNA TRIPLE PAK or VOQUEZNA DUAL PAK is not recommended in patients with severe renal impairment (eGFR < 30 mL/min) [see Dosage and Administration (2.3) and Clinical Pharmacology (12.3)].

8.7 Hepatic Impairment

No dosage adjustment of VOQUEZNA TRIPLE PAK or VOQUEZNA DUAL PAK is recommended in patients with mild hepatic impairment (Child-Pugh A). Use of VOQUEZNA TRIPLE PAK or VOQUEZNA DUAL PAK is not recommended in patients with moderate to severe hepatic impairment (Child-Pugh B or C) [see Dosage and Administration (2.4) and Clinical Pharmacology (12.3)].

10 OVERDOSAGE

No information is available on accidental overdosage of VOQUEZNA TRIPLE PAK or VOQUEZNA DUAL PAK in humans.

In case of an overdose, patients should contact a physician, poison control center, or emergency room. The available overdosage information for each of the individual components in VOQUEZNA TRIPLE PAK and VOQUEZNA DUAL PAK are summarized below:

Vonoprazan

There have been no reports of overdose with vonoprazan. In clinical studies, a single dose of 120 mg resulted in no serious adverse reactions. Vonoprazan is not removed from the circulation by hemodialysis. If overdose occurs, treatment should be symptomatic and supportive.

Amoxicillin

In case of amoxicillin overdosage, discontinue medication, treat symptomatically and institute supportive measures as needed. A prospective study of 51 pediatric patients at a poison-control center suggested that overdosages of less than 250 mg/kg of amoxicillin are not associated with significant clinical symptoms.

Interstitial nephritis resulting in oliguric renal failure has been reported in a small number of patients after overdosage with amoxicillin.

Crystalluria, in some cases leading to renal failure, has also been reported after amoxicillin overdosage in adult and pediatric patients. In case of overdosage, adequate fluid intake and diuresis should be maintained to reduce the risk of amoxicillin crystalluria.

Renal impairment appears to be reversible with cessation of drug administration. High blood levels may occur more readily in patients with impaired renal function because of decreased renal clearance of amoxicillin. Amoxicillin can be removed from circulation by hemodialysis.

Clarithromycin

Overdosage of clarithromycin can cause gastrointestinal symptoms such as abdominal pain, vomiting, nausea, and diarrhea.

Treat adverse reactions accompanying overdosage by the prompt elimination of unabsorbed drug and supportive measures. As with other macrolides, clarithromycin serum concentrations are not expected to be appreciably affected by hemodialysis or peritoneal dialysis.

11 DESCRIPTION

VOQUEZNA TRIPLE PAK contains vonoprazan tablets, 20 mg, amoxicillin capsules, 500 mg, and clarithromycin tablets, 500 mg for oral administration. VOQUEZNA DUAL PAK contains vonoprazan tablets, 20 mg and amoxicillin capsules, 500 mg for oral administration.

Vonoprazan Tablets

Vonoprazan (as the fumarate), is a potassium-competitive acid blocker (PCAB). Chemically, it is 1H-pyrrole-3-methanamine, 5-(2-fluorophenyl)-N-methyl-1-(3-pyridinylsulfonyl)-, (2E)-2-butenedioate (1:1). Its empirical formula is C17H16FN3O2S∙C4H4O4 with a molecular weight of 461.5. Vonoprazan has the following structure:

Vonoprazan fumarate is white to nearly white crystals or crystalline powder which melts at 194.8°C. Vonoprazan fumarate is soluble in dimethyl sulfoxide; sparingly soluble in N,N–dimethylacetamide, slightly soluble in N,N-dimethylformamide, methanol, and water; very slightly soluble in ethanol (99.5); and practically insoluble in 2-propanol, acetone, 1-octanol, and acetonitrile.

Each film-coated tablet contains 20 mg of vonoprazan, present as 26.72 mg of vonoprazan fumarate and the following inactive ingredients: ascorbic acid, croscarmellose sodium, ferric oxide red, fumaric acid, hydroxypropyl cellulose, hypromellose, magnesium stearate, mannitol, microcrystalline cellulose, polyethylene glycol 8000, and titanium dioxide.

Amoxicillin Capsules

Amoxicillin is a penicillin class antibacterial, with a broad spectrum of bactericidal activity against many gram-positive and gram-negative microorganisms. Chemically it is (2S, 5R, 6R)-6-[(R)-(-)-2-amino-2-(p-hydroxyphenyl) acetamido]-3,3-dimethyl-7-oxo-4-thia-1-azabicyclo [3.2.0] heptane-2-carboxylic acid trihydrate. The molecular formula is C16H19N3O5S ∙ 3H2O and the molecular weight is 419.45. Amoxicillin has the following structure:

Each amoxicillin capsule, with yellow opaque cap and body, contains 500 mg amoxicillin as the trihydrate. Inactive ingredients: Capsule shells – ammonium hydroxide, black ferric oxide, gelatin, potassium hydroxide, propylene glycol, shellac, titanium dioxide, and yellow ferric oxide; Capsule contents – magnesium stearate and microcrystalline cellulose.

Meets USP Dissolution Test 2.

Clarithromycin Tablets

Clarithromycin is a semi-synthetic macrolide antimicrobial for oral use. Chemically, it is 6-O-methylerythromycin. The molecular formula is C38H69NO13, and the molecular weight is 747.96. Clarithromycin has the following structure:

Clarithromycin is a white to off-white crystalline powder. It is soluble in acetone, slightly soluble in methanol, ethanol, and acetonitrile, and practically insoluble in water.

Each clarithromycin tablet contains 500 mg of clarithromycin and the following inactive ingredients: croscarmellose sodium, hypromellose, magnesium stearate, microcrystalline cellulose, polyethylene glycol, polysorbate 80, povidone, talc, and titanium dioxide.

12 CLINICAL PHARMACOLOGY

12.1 Mechanism of Action

Vonoprazan suppresses basal and stimulated gastric acid secretion at the secretory surface of the gastric parietal cell through inhibition of the H^+, K^+-ATPase enzyme system in a potassium competitive manner. Because this enzyme is regarded as the acid (proton) pump within the parietal cell, vonoprazan has been characterized as a type of gastric proton-pump inhibitor, in that it blocks the final step of acid production. Vonoprazan does not require activation by acid. Vonoprazan may selectively concentrate in the parietal cells in both the resting and stimulated states. Vonoprazan binds to the active proton pumps in a noncovalent and reversible manner.

Amoxicillin is an antibacterial drug. Clarithromycin is a macrolide antimicrobial drug [see Microbiology (12.4)].

Acid suppression enhances the replication of H. pylori bacteria and the stability and effectiveness of antimicrobials in the treatment of H. pylori infection.

12.2 Pharmacodynamics

Vonoprazan

Antisecretory Activity

Following a single 20 mg dose of vonoprazan, the onset of the antisecretory effect as measured by intragastric pH occurs within 2 to 3 hours. The elevated intragastric pH compared to placebo is maintained for over 24-hours after dosing. The inhibitory effect of vonoprazan on acid secretion increases with repeated daily dosing and antisecretory effect reached steady state by Day 4 with a mean (SD) 24-hour intragastric pH of 6.0 (1.5) following 20 mg once daily dose (not an approved recommended dosage). The antisecretory effect of vonoprazan decreases following drug discontinuation although intragastric pH remained elevated compared to placebo for 24 to 48 hours following the dose on Day 7.

Cardiac Electrophysiology

At a dose 6 times the maximum recommended dose, vonoprazan does not prolong the QT interval to any clinically relevant extent.

Serum Gastrin Effects

In clinical trials conducted in adult patients with erosive esophagitis, treatment with vonoprazan increased baseline serum gastrin concentrations. Mean gastrin levels remained elevated with the recommended daily dose of vonoprazan for the treatment of erosive esophagitis and the mean serum gastrin levels returned to normal within 4 weeks of discontinuation of treatment.

Increased gastrin causes enterochromaffin-like cell hyperplasia and increased serum CgA levels. The increased CgA levels may cause false positive results in diagnostic investigations for neuroendocrine tumors [see Warnings and Precautions (5.1) and Drug Interactions (7)].

12.3 Pharmacokinetics

Pharmacokinetic (PK) parameters for vonoprazan 20 mg after a single dose (not an approved recommended dosage) and at steady state following twice daily administration are summarized in Table 8.

Table 8: Mean (%CV) Pharmacokinetic Parameters for Vonoprazan Following a Single Dose or at Steady State Following Twice Daily Dosing
PK Parameter | Single Dose (N=10) | Steady State (N=32)
Tmax (h), median (range) | 2.5 (1.0-4.0) | 3.0 (1.0-6.0)
Cmax (ng/mL) | 25.2 (39.7) | 37.8 (36.1)
AUC0-12h (ng*hr/mL) | 154.8 (25.2) | 272.5 (30.5)
t1/2 (h) | 7.1 (10.1) | 6.8 (22.7)
CL/F (L/h) | 97.3 (36.3) | 81.3 (35.7)
Vz/F (L) | 1001 (39.6) | 782.7 (34.4)
Cmax = Maximum plasma concentration; AUC0-12h = Area under the plasma concentration-time curve from time 0 to the end of the 12-hour dosing interval; Tmax = Time to reach Cmax; t1/2 = Elimination half-life, CL/F = Apparent oral clearance, Vz/F = Apparent oral volume of distribution.

Vonoprazan

Absorption

Vonoprazan exhibits time independent pharmacokinetics and steady state concentrations are achieved by Day 3 to 4. After multiple doses of vonoprazan ranging from 10 mg (0.5 times the lowest approved recommended single dosage) to 40 mg (2 times the highest approved recommended single dosage) once daily for 7 days in healthy subjects, Cmax and AUC values for vonoprazan increased in an approximately dose-proportional manner.

Steady state mean plasma exposure of vonoprazan following 20 mg twice daily dosing (AUC0-12h = 273 hr*ng/mL, N=10) was approximately 1.8-fold higher compared to Day 1 (AUC0-12h = 155 hr*ng/mL, N=10).

Effect of Food:

In a food effect study in healthy subjects (N=24) receiving vonoprazan 20 mg, a high-fat meal resulted in a 5% increase in Cmax, a 15% increase in AUC, and a delay in median Tmax of 2 hours. These changes are not considered to be clinically significant.

Distribution

Plasma protein binding of vonoprazan ranged from 85 to 88% in healthy subjects and was independent of concentration from 0.1 to 10 mcg/mL.

Elimination

Metabolism:

Vonoprazan is metabolized to inactive metabolites via multiple pathways by a combination of cytochrome P450 (CYP) isoforms (predominantly CYP3A4/5, CYP2C19, CYP2D6, and CYP2B6) along with sulfo- and glucuronosyl-transferases. CYP2C19 and CYP2D6 polymorphisms have been evaluated in clinical studies and there were no clinically meaningful differences in the pharmacokinetics of vonoprazan based on either CYP2C19 or CYP2D6 metabolizer status.

Excretion:

Following oral administration of radiolabeled vonoprazan, approximately 67% of the radiolabeled dose (8% as unchanged vonoprazan) was recovered in urine and 31% (1.4% as unchanged vonoprazan) was recovered in feces.

Specific Populations

Sex, Race or Ethnicity:

There were no clinically significant differences in the pharmacokinetics of vonoprazan based on sex or race/ethnicity.

Patients with Renal Impairment

The pharmacokinetics of vonoprazan administered as a single 20 mg dose in patients with mild (N=8), moderate (N=8), or severe (N=8) renal impairment were compared to those with normal renal function (N=13). Compared to subjects with normal renal function, systemic exposure (AUC∞) was 1.7-, 1.3-, and 2.4-times greater in patients with mild, moderate, and severe renal impairment, respectively. In subjects requiring dialysis (N=8), AUC∞ estimates were 1.3-fold greater compared to estimates from subjects with normal renal function [see Dosage and Administration (2.3)]. Protein binding of vonoprazan is not affected by impaired renal function. In patients requiring dialysis, vonoprazan was present in the dialysate and represented 0.94% of the dose administered.

Patients with Hepatic Impairment

The pharmacokinetics of vonoprazan administered as a single 20 mg dose in patients with mild [Child-Pugh Class A (N=8)], moderate [Child-Pugh Class B (N=8)], or severe [Child-Pugh Class C (N=6)] hepatic impairment were compared to those with normal hepatic function (N=12). Compared to subjects with normal hepatic function, systemic exposure (AUC∞) of vonoprazan was 1.2-, 2.4-, and 2.6-times greater in patients with mild, moderate, and severe hepatic impairment, respectively. [see Dosage and Administration (2.4)]. Protein binding of vonoprazan is not affected by impaired hepatic function.

Drug Interaction Studies

In vitro studies:

Cytochrome P450 (CYP450) Enzymes:

In vitro studies have shown that vonoprazan directly and time-dependently inhibits CYP2B6, CYP2C19, and CYP3A4/5.

Transporter Systems:

Vonoprazan inhibits multidrug and toxin extrusion protein 1 (MATE1) and organic cation transporter 1 (OCT1), but only at concentrations higher than clinically relevant.

Clinical Studies:

Combination Therapy with Vonoprazan, Amoxicillin, and Clarithromycin:

When vonoprazan 20 mg, amoxicillin 750 mg, and clarithromycin 400 mg were co-administered twice daily for 7 days (N=11), there was no effect on pharmacokinetics of amoxicillin compared to administration of amoxicillin alone. However, vonoprazan Cmax and AUC0-12h increased by 87% and 85%, respectively, and clarithromycin, Cmax and AUC0-12h increased by 64% and 45%, respectively, compared to administration of each component alone.

Effect of Vonoprazan on CYP3A4 Substrates:

When a single oral dose of midazolam 2 mg was administered following vonoprazan 20 mg twice daily for 7 days (N=20), midazolam AUC∞ increased 93% compared to administration of midazolam alone.

Effect of CYP3A Inhibitors on Vonoprazan:

When a single 40 mg (2 times the highest approved recommended single dosage) dose of vonoprazan was administered with clarithromycin 500 mg twice daily for 7 days (N=16), vonoprazan AUC∞ increased 58% compared to administration of vonoprazan alone.

Model-Informed Approaches:

Effect of CYP3A Inducers on Vonoprazan:

Vonoprazan exposures are predicted to be 80% lower when co-administered with a strong CYP3A4 inducer such as rifampicin and 50% lower when co-administered with a moderate CYP3A4 inducer such as efavirenz.

Amoxicillin

Absorption

Amoxicillin is stable in the presence of gastric acid and is rapidly absorbed after oral administration. Orally administered doses of 500-mg amoxicillin capsules result in average peak blood levels 1 to 2 hours after administration in the range of 5.5 mcg/mL to 7.5 mcg/mL, respectively.

Distribution

Amoxicillin diffuses readily into most body tissues and fluids, with the exception of brain and spinal fluid, except when meninges are inflamed. In blood serum, amoxicillin is approximately 20% protein-bound. Following a 1-gram dose and utilizing a special skin window technique to determine levels of the antibacterial, it was noted that therapeutic levels were found in the interstitial fluid.

Metabolism and Excretion

The half-life of amoxicillin is 61.3 minutes. Approximately 60% of an orally administered dose of amoxicillin is excreted in the urine within 6 to 8 hours. Detectable serum levels are observed up to 8 hours after an orally administered dose of amoxicillin. Since most of the amoxicillin is excreted unchanged in the urine, its excretion can be delayed by concurrent administration of probenecid.

Clarithromycin

Absorption

For a single 500 mg dose of clarithromycin, food slightly delays the onset of clarithromycin absorption, increasing the peak time from approximately 2 to 2.5 hours. Food also increases the clarithromycin peak plasma concentration by about 24%, but does not affect the extent of clarithromycin bioavailability. Food does not affect the onset of formation of the active metabolite, 14-OH clarithromycin or its peak plasma concentration but does slightly decrease the extent of metabolite formation, indicated by an 11% decrease in AUC. Therefore, clarithromycin may be given without regard to food. In non-fasting healthy human subjects (males and females), peak plasma concentrations were attained within 2 to 3 hours after oral dosing.

Distribution

Clarithromycin and the 14-OH clarithromycin metabolite distribute readily into body tissues and fluids. There are no data available on cerebrospinal fluid penetration. Because of high intracellular concentrations, tissue concentrations are higher than serum concentrations.

Metabolism and Elimination

Steady-state peak plasma clarithromycin concentrations were attained within 3 days and were 3 mcg/mL to 4 mcg/mL with a 500 mg dose administered every 8 hours to 12 hours. The elimination half-life of clarithromycin was 5 hours to 7 hours with 500 mg administered every 8 hours to 12 hours. The nonlinearity of clarithromycin pharmacokinetics is slight at the recommended doses of 500 mg administered every 8 hours to 12 hours. With a 500 mg every 8 hours to 12 hours dosing, the peak steady-state concentration of 14-OH clarithromycin is slightly higher (up to 1 mcg/mL), and its elimination half-life is about 7 hours to 9 hours. With any of these dosing regimens, the steady-state concentration of this metabolite is generally attained within 3 days to 4 days.

After a 500 mg tablet every 12 hours, the urinary excretion of clarithromycin is approximately 30%. The renal clearance of clarithromycin is, however, relatively independent of the dose size and approximates the normal glomerular filtration rate. The major metabolite found in urine is 14-OH clarithromycin, which accounts for an additional 10% to 15% of the dose with a 500 mg tablet administered every 12 hours.

Patients with Hepatic Impairment

The steady-state concentrations of clarithromycin in subjects with impaired hepatic function did not differ from those in normal subjects; however, the 14-OH clarithromycin concentrations were lower in the hepatically impaired subjects. The decreased formation of 14-OH clarithromycin was at least partially offset by an increase in renal clearance of clarithromycin in the subjects with impaired hepatic function when compared to healthy subjects.

Patients with Renal Impairment

The pharmacokinetics of clarithromycin were also altered in subjects with impaired renal function.

Drug Interaction Studies

Fluconazole:

Following administration of fluconazole 200 mg daily and clarithromycin 500 mg twice daily to 21 healthy volunteers, the steady-state clarithromycin Cmin and AUC increased 33% and 18%, respectively. Clarithromycin exposures were increased and steady-state concentrations of 14-OH clarithromycin were not significantly affected by concomitant administration of fluconazole.

Colchicine:

When a single dose of colchicine 0.6 mg was administered with clarithromycin 250 mg twice daily for 7 days, the colchicine Cmax increased 197% and the AUC0-∞ increased 239% compared to administration of colchicine alone.

Atazanavir:

Following administration of clarithromycin (500 mg twice daily) with atazanavir (400 mg once daily), the clarithromycin AUC increased 94%, the 14-OH clarithromycin AUC decreased 70%, and the atazanavir AUC increased 28%.

Ritonavir:

Concomitant administration of clarithromycin and ritonavir (N=22) resulted in a 77% increase in clarithromycin AUC and a 100% decrease in the AUC of 14-OH clarithromycin.

Saquinavir:

Following administration of clarithromycin (500 mg twice daily) and saquinavir (soft gelatin capsules, 1200 mg tid) to 12 healthy volunteers, the steady-state saquinavir AUC and Cmax increased 177% and 187% respectively compared to administration of saquinavir alone. Clarithromycin AUC and Cmax increased 45% and 39% respectively, whereas the 14-OH clarithromycin AUC and Cmax decreased 24% and 34% respectively, compared to administration with clarithromycin alone.

Didanosine:

Simultaneous administration of clarithromycin tablets and didanosine to 12 HIV-infected adult patients resulted in no statistically significant change in didanosine pharmacokinetics.

Zidovudine:

Following administration of clarithromycin 500 mg tablets twice daily with zidovudine 100 mg every 4 hours, the steady-state zidovudine AUC decreased 12% compared to administration of zidovudine alone (N=4). Individual values ranged from a decrease of 34% to an increase of 14%. When clarithromycin tablets were administered two to four hours prior to zidovudine, the steady-state zidovudine Cmax increased 100% whereas the AUC was unaffected (N=24).

Omeprazole:

Clarithromycin 500 mg every 8 hours was given in combination with omeprazole 40 mg daily to healthy adult subjects. The steady-state plasma concentrations of omeprazole were increased (Cmax, AUC0-24, and t½ increases of 30%, 89%, and 34%, respectively), by the concomitant administration of clarithromycin.

The plasma levels of clarithromycin and 14-OH clarithromycin were increased by the concomitant administration of omeprazole. For clarithromycin, the mean Cmax was 10% greater, the mean Cmin was 27% greater, and the mean AUC0-8 was 15% greater when clarithromycin was administered with omeprazole than when clarithromycin was administered alone. Similar results were seen for 14-OH clarithromycin, the mean Cmax was 45% greater, the mean Cmin was 57% greater, and the mean AUC0-8 was 45% greater. Clarithromycin concentrations in the gastric tissue and mucus were also increased by concomitant administration of omeprazole.

Table 9: Clarithromycin Tissue Concentrations 2 hours after Dose (mcg/mL)/(mcg/g)
Treatment | N | Antrum | Fundus | N | Mucus
Clarithromycin | 5 | 10.48 ± 2.01 | 20.81 ± 7.64 | 4 | 4.15 ± 7.74
Clarithromycin + Omeprazole | 5 | 19.96 ± 4.71 | 24.25 ± 6.37 | 4 | 39.29 ± 32.79

Theophylline:

In two studies in which theophylline was administered with clarithromycin (a theophylline sustained-release formulation was dosed at either 6.5 mg/kg or 12 mg/kg together with 250 or 500 mg q12h clarithromycin), the steady-state levels of Cmax, Cmin, and the AUC of theophylline increased about 20%.

Midazolam:

When a single dose of midazolam was co-administered with clarithromycin tablets (500 mg twice daily for 7 days), midazolam AUC increased 174% after intravenous administration of midazolam and 600% after oral administration.

12.4 Microbiology

Mechanism of Action

Amoxicillin is similar to penicillin in its bactericidal action against susceptible bacteria during the stage of active multiplication. It acts through the inhibition of cell wall biosynthesis that leads to the death of the bacteria.

Clarithromycin exerts its antibacterial activity by binding to the 50S ribosomal subunit of susceptible bacteria resulting in inhibition of protein synthesis.

Resistance

Resistance to amoxicillin is mediated primarily through enzymes called beta-lactamases that cleave the beta-lactam ring of amoxicillin, rendering it inactive.

The major routes of clarithromycin resistance are modification of the 23S rRNA in the 50S ribosomal subunit to insensitivity or drug efflux pumps. Beta-lactamase production should have no effect on clarithromycin activity.

If H. pylori is not eradicated after treatment with clarithromycin-containing combination regimens, patients may develop clarithromycin resistance in H. pylori isolates. Therefore, for patients who fail therapy, clarithromycin susceptibility testing should be done, if possible.

Antimicrobial Activity

Culture and sensitivity testing of bacteria are not routinely performed to establish the diagnosis of H. pylori infection [see Clinical Studies (14)]. The following in vitro data are available, but their clinical significance is unknown. Clarithromycin and amoxicillin are active in vitro against most isolates of H. pylori.

Susceptibility Testing

For specific information regarding susceptibility test interpretive criteria and associated test methods and quality control standards recognized by FDA for this drug, please see: www.fda.gov/medwatch).

Effects on Gastrointestinal Microbial Ecology

Decreased gastric acidity due to any means, increases gastric counts of bacteria normally present in the gastrointestinal tract. Vonoprazan decreases gastric acidity, VOQUEZNA TRIPLE PAK or VOQUEZNA DUAL PAK may lead to a slightly increased risk of gastrointestinal infections due to pathogens such as Salmonella and Campylobacter and, in hospitalized patients, possibly also due to C. difficile.

13 NONCLINICAL TOXICOLOGY

13.1 Carcinogenesis, Mutagenesis, Impairment of Fertility

No adequate or well-controlled long-term studies have been performed to evaluate the effect of VOQUEZNA TRIPLE PAK and VOQUEZNA DUAL PAK on carcinogenesis, mutagenesis, or impairment of fertility.

Vonoprazan

Carcinogenicity

In a 24-month carcinogenicity study in mice, vonoprazan at daily oral doses of 6, 20, 60, and 200 mg/kg/day (approximately 0.4, 4, 19, and 93 times the MRHD based on AUC) produced hyperplasia of neuroendocrine cells, gastropathy and benign and/or malignant neuroendocrine cell tumors (carcinoids) in the stomach at all doses in males and at 60 mg/kg/day and greater in females. In liver, increased incidences of hepatocellular adenoma and carcinomas were observed at doses of 20 mg/kg/day and greater in males and 60 mg/kg/day and greater in females.

In a 24-month carcinogenicity study in Sprague-Dawley rats, vonoprazan at daily oral doses of 5, 15, 50, and 150 mg/kg/day (approximately 0.6, 4, 19, and 65 times the MRHD based on AUC) produced benign and/or malignant neuroendocrine cell tumors in the stomach in both male and female rats at doses of 5 mg/kg/day or more. Increased incidence of hepatocellular adenoma and carcinomas and hepatocholangiocellular adenomas and carcinomas were observed at doses of 50 and 150 mg/kg/day.

In both mice and rats, neuroendocrine tumors in the stomach occurred in association with neuroendocrine hyperplasia and gastropathy in the stomach and increased plasma gastrin concentrations that are consistent with inhibition of gastric acid secretion. Carcinoid tumors have also been observed in rats subjected to fundectomy or long-term treatment with proton pump inhibitors or high doses of H2-receptor antagonists.

Mutagenesis

Vonoprazan was negative for mutagenicity in the in vitro Ames test, in an in vitro clastogenicity assay in Chinese Hamster cells and in vivo in a rat bone marrow micronucleus study.

Impairment of Fertility

Vonoprazan at oral doses up to 300 mg/kg/day in rats (approximately 133 times the MRHD based on AUC from a separate study in nonpregnant animals administered the same dose) was found to have no effect on fertility and reproductive performance. Elongation of the estrous cycle was observed in rats at doses equivalent to 133 times the MRHD based on AUC.

Amoxicillin

Carcinogenicity

Long-term studies in animals have not been performed to evaluate carcinogenic potential.

Mutagenesis

Studies to detect mutagenic potential of amoxicillin alone have not been conducted; however, the following information is available from tests on a 4:1 mixture of amoxicillin and potassium clavulanate. Amoxicillin and potassium clavulanate were non-mutagenic in the Ames bacterial mutation assay, and the yeast gene conversion assay. Amoxicillin and potassium clavulanate were weakly positive in the mouse lymphoma assay, but the trend toward increased mutation frequencies in this assay occurred at doses that were also associated with decreased cell survival. Amoxicillin and potassium clavulanate were negative in the mouse micronucleus test and in the dominant lethal assay in mice. Potassium clavulanate alone was tested in the Ames bacterial mutation assay and in the mouse micronucleus test and was negative in each of these assays.

Impairment of Fertility

In a multi-generation reproduction study in rats, no impairment of fertility or other adverse reproductive effects were seen at doses up to 500 mg/kg (approximately 1.6 times the human dose in mg/m^2).

Clarithromycin

Mutagenesis

The following in vitro mutagenicity tests have been conducted with clarithromycin:

- Salmonella/Mammalian Microsomes Test
- Bacterial Induced Mutation Frequency Test
- In Vitro Chromosome Aberration Test
- Rat Hepatocyte DNA Synthesis Assay
- Mouse Lymphoma Assay
- Mouse Dominant Lethal Study
- Mouse Micronucleus Test

All tests had negative results except the in vitro chromosome aberration test which was positive in one test and negative in another. In addition, a bacterial reverse-mutation test (Ames test) has been performed on clarithromycin metabolites with negative results.

Impairment of Fertility

Fertility and reproduction studies have shown that daily doses of up to 160 mg/kg/day to male and female rats caused no adverse effects on the estrous cycle, fertility, parturition, or number and viability of offspring. Plasma levels in rats after 150 mg/kg/day were twice the human serum levels.

Testicular atrophy occurred in rats at doses 7 times, in dogs at doses 3 times, and in monkeys at doses 8 times greater than the maximum human daily dose (on a BSA comparisons).

13.2 Animal Toxicology and/or Pharmacology

Clarithromycin

Corneal opacity occurred in dogs at doses 12 times and in monkeys at doses 8 times greater than the maximum human daily dose (on BSA comparisons). Lymphoid depletion occurred in dogs at doses 3 times greater than and in monkeys at doses 2 times greater than the maximum human daily dose (on BSA comparisons).

14 CLINICAL STUDIES

The effectiveness and safety of VOQUEZNA TRIPLE PAK and VOQUEZNA DUAL PAK were evaluated in a randomized, controlled, double-blind triple therapy/open-label dual therapy study conducted in the United States and Europe in treatment-naïve H. pylori-positive adult patients with at least one clinical condition: dyspepsia lasting at least 2 weeks, functional dyspepsia, recent/new diagnosis of peptic ulcer, peptic ulcer not treated for H. pylori infection, or a stable dose of long-term NSAID treatment (NCT04167670). Patients were randomized 1:1:1 to vonoprazan 20 mg twice daily plus amoxicillin 1,000 mg twice daily plus clarithromycin 500 mg twice daily (VOQUEZNA TRIPLE PAK) or vonoprazan 20 mg twice daily plus amoxicillin 1,000 mg three times daily (VOQUEZNA DUAL PAK) or lansoprazole 30 mg twice daily plus amoxicillin 1,000 mg twice daily plus clarithromycin 500 mg twice daily (LAC) administered for 14 consecutive days.

H. pylori infection at baseline was defined as positive by ^13C urea breath test (UBT) and follow-up upper endoscopy (culture or histology). H. pylori eradication was confirmed with a negative ^13C UBT test-of-cure at ≥ 27 days post-therapy. Patients with negative test results were considered treatment successes. Patients who tested positive for H. pylori infection and patients with missing results from the test-of-cure visit were considered treatment failures.

VOQUEZNA TRIPLE PAK and VOQUEZNA DUAL PAK were shown to be noninferior to LAC in patients who did not have a clarithromycin or amoxicillin resistant strain of H. pylori at baseline. VOQUEZNA TRIPLE PAK and VOQUEZNA DUAL PAK were shown to be superior to LAC in patients who had a clarithromycin resistant strain of H. pylori at baseline and in the overall population.

H. pylori eradication rates are shown in Table 10 for VOQUEZNA TRIPLE PAK and VOQUEZNA DUAL PAK compared to LAC.

Table 10: Eradication Rates of H. pylori in Patients Receiving VOQUEZNA TRIPLE PAK, VOQUEZNA DUAL PAK, or LAC at ≥27 Days Post-therapy - mITT
 | VOQUEZNA TRIPLE PAK | VOQUEZNA DUAL PAK | LAC
 | % (n) | % (n) | % (n)
Patients with H. pylori infection who did not have a clarithromycin or amoxicillin resistant strain at baseline [Clarithromycin resistant strains of H. pylori were considered those with an MIC ≥ 1 µg/mL; amoxicillin resistant strains were considered those with an MIC > 0.125 µg/mL.] | 84.7 (222) | 78.5 (208) | 78.8 (201)
Treatment Difference from LAC (95% CI) | 5.9 [p<0.0001 for test of non-inferiority versus LAC.] (-0.8, 12.6) | -0.3 [p<0.01 for test of non-inferiority versus LAC.] (-7.4, 6.8)
All randomized patients with H. pylori infection at baseline | 80.8 (273) | 77.2 (250) | 68.5 (226)
Treatment Difference from LAC (95% CI) | 12.3 [p=0.0003 for test of superiority versus LAC.] (5.7, 18.8) | 8.7 [p=0.01 for test of superiority versus LAC.] (1.9, 15.4)
Patients with H. pylori infection who had a clarithromycin resistant strain of H. pylori at baseline | 65.8 (48) | 69.6 (39) | 31.9 (23)
Treatment Difference from LAC (95% CI) | 33.8 [p<0.0001 for test of superiority versus LAC.] (17.7, 48.1) | 37.7 (20.5, 52.6)
LAC = lansoprazole, amoxicillin, clarithromycin triple therapy regimen; CI = confidence interval calculated via the Miettinen and Nurminen method
Modified intent to treat (mITT) population: Patients were included in the mITT analysis if they had documented H. pylori infection at baseline.

16 HOW SUPPLIED/STORAGE AND HANDLING

VOQUEZNA TRIPLE PAK is a co-package containing:

- Vonoprazan Tablets, 20 mg: pale red, oval, film-coated tablets debossed V20 on one side and plain on the other side.
- Amoxicillin Capsules, 500 mg: yellow, opaque, hard gelatin capsules imprinted with AMOX 500 on one side and GG 849 on the other side.
- Clarithromycin Tablets, 500 mg: white, oval, film-coated tablets debossed GG C9 on one side and plain on the other side.

Vonoprazan tablets, amoxicillin capsules, and clarithromycin tablets are supplied in separate blister cavities within the same blister card.

Each unit of use carton (NDC 81520-255-14) contains 56 tablets and 56 capsules divided into 14 daily dose blister cards.

Each daily blister card contains two vonoprazan tablets (20 mg each), four amoxicillin capsules (500 mg each), and two clarithromycin tablets (500 mg each), and indicates which tablets and capsules need to be taken in the morning and evening.

STORAGE AND HANDLING

Store between 20°C and 25°C (68°F and 77°F). Brief exposure to 15°C to 30°C (59°F to 86°F) permitted (see USP Controlled Room Temperature). Protect from light.

VOQUEZNA DUAL PAK is a co-package containing:

- Vonoprazan Tablets, 20 mg: pale red, oval, film-coated tablets debossed V20 on one side and plain on the reverse side.
- Amoxicillin Capsules, 500 mg: yellow, opaque, hard gelatin capsules imprinted with AMOX 500 on one side and GG 849 on the other side.

Vonoprazan tablets and amoxicillin capsules are supplied in separate blister cavities within the same blister card.

Each unit of use carton (NDC 81520-250-14) contains 28 tablets and 84 capsules divided into 14 daily dose blister cards.

Each daily blister card contains two vonoprazan tablets (20 mg each) and six amoxicillin capsules (500 mg each) and indicates which tablets and capsules need to be taken in the morning, mid-day, and evening.

Store between 20°C and 25°C (68°F and 77°F). Brief exposure to 15°C to 30°C (59°F to 86°F) permitted (see USP Controlled Room Temperature).

17 PATIENT COUNSELING INFORMATION

Hypersensitivity Reactions

Patients should be aware that VOQUEZNA TRIPLE PAK and VOQUEZNA DUAL PAK can cause allergic reactions in some individuals. Advise the patient to call their healthcare provider immediately if they develop a new rash, urticaria, drug eruptions, swelling of the face, difficulty in breathing or other symptoms of allergic reactions [see Warnings and Precautions (5.1) and Adverse Reactions (6.2)].

Acute Tubulointerstitial Nephritis

Advise patients to call their healthcare provider if they experience signs and/or symptoms associated with acute tubulointerstitial nephritis [see Warnings and Precautions (5.1)].

Severe Cutaneous Adverse Reactions

Advise patients about the signs and symptoms of serious skin manifestations. Instruct patients to stop taking VOQUEZNA TRIPLE PAK or VOQUEZNA DUAL PAK immediately and promptly report the first signs or symptoms of skin rash, mucosal lesions, or any other sign of hypersensitivity [see Warnings and Precautions (5.1) and Adverse Reactions (6.2)].

Drug Interactions

Advise patients that VOQUEZNA TRIPLE PAK or the individual components of VOQUEZNA TRIPLE PAK may interact with some drugs; therefore, advise patients to report to their healthcare provider the use of any other medications including natural substitutes and nutritional supplements.

Diarrhea

Advise patients that diarrhea is a common problem caused by antibacterials including amoxicillin and clarithromycin, and it usually ends when the drugs are stopped. However, rarely after receiving treatment with VOQUEZNA TRIPLE PAK or VOQUEZNA DUAL PAK, patients can develop watery and bloody stools (with or without stomach cramps and fever) even as late as 2 or more months after having taken their last dose. If this occurs, instruct patients to contact their healthcare provider as soon as possible [see Warnings and Precautions (5.1)].

Embryo-Fetal Toxicity

Advise pregnant patients and females of reproductive potential that if pregnancy occurs while taking VOQUEZNA TRIPLE PAK, there is a potential risk to the fetus due to the clarithromycin component [see Warnings and Precautions (5.2) and Use in Specific Populations (8.1)].

Advise patients who are exposed to VOQUEZNA TRIPLE PAK or VOQUEZNA DUAL PAK during pregnancy to contact Phathom Pharmaceuticals, Inc. at 1-888-775-7428.

Pregnancy

Advise patients that there is a pregnancy exposure registry that monitors pregnancy outcomes in women exposed to VOQUEZNA TRIPLE PAK or VOQUEZNA DUAL PAK during pregnancy [see Use in Specific Populations (8.1)].

Lactation

Advise breastfeeding women to monitor their infants for diarrhea, vomiting, and rash [see Use in Specific Populations (8.2)].

Infertility

Advise males of reproductive potential that VOQUEZNA TRIPLE PAK may impair fertility [see Use in Specific Populations (8.3)].

Potential for Dizziness, Vertigo and Confusion

There are no data on the effect of VOQUEZNA TRIPLE PAK on the ability to drive or use machines. However, counsel patients regarding the potential for dizziness, vertigo, confusion, and disorientation, which may occur with clarithromycin, a component of VOQUEZNA TRIPLE PAK. The potential for these adverse reactions should be taken into account before patients drive or use machines.

Important Administration Instructions for VOQUEZNA TRIPLE PAK and VOQUEZNA DUAL PAK

- Take with or without food [see Dosage and Administration (2) and Clinical Pharmacology (12.3)].
- Missed doses: Advise patients that if a dose of VOQUEZNA TRIPLE PAK or VOQUEZNA DUAL PAK is missed, administer as soon as possible within 4 hours after the missed dose. If more than 4 hours have passed, skip the missed dose and administer the next dose on the regularly scheduled time. It is important for patients to complete the entire course of therapy [see Dosage and Administration (2)].
- Counsel patients to continue the full course of VOQUEZNA TRIPLE PAK or VOQUEZNA DUAL PAK regardless of whether or not their symptoms improve. Counsel patients that treatment of H. pylori infection is important due to its association with stomach ulcers, atrophic gastritis, and increased risk of gastric cancer.

Antibacterial Resistance

Patients should be counseled that antibacterial drugs including VOQUEZNA TRIPLE PAK or VOQUEZNA DUAL PAK should only be used to treat bacterial infections. They do not treat viral infections (e.g., the common cold). When VOQUEZNA TRIPLE PAK or VOQUEZNA DUAL PAK is prescribed to treat a bacterial infection, patients should be told that although it is common to feel better early in the course of therapy, the medication should be taken exactly as directed. Skipping doses or not completing the full course of therapy may (1) decrease the effectiveness of the immediate treatment and (2) increase the likelihood that bacteria will develop resistance and will not be treatable by VOQUEZNA TRIPLE PAK, VOQUEZNA DUAL PAK or other antibacterial drugs in the future [see Warnings and Precautions (5.1)].

VOQUEZNA TRIPLE PAK and VOQUEZNA DUAL PAK are distributed by Phathom Pharmaceuticals, Inc., Buffalo Grove, IL 60089, U.S.A.

Vonoprazan Tablets are manufactured for Phathom Pharmaceuticals, Inc., Buffalo Grove, IL 60089, U.S.A.

Amoxicillin Capsules and Clarithromycin Tablets are manufactured for Sandoz Inc., Princeton, NJ 08540, U.S.A.

VOQUEZNA, VOQUEZNA TRIPLE PAK, VOQUEZNA DUAL PAK, the VOQUEZNA logo, and Phathom Pharmaceuticals are registered trademarks of Phathom Pharmaceuticals, Inc.

© 2025 Phathom Pharmaceuticals, Inc. All rights reserved.

VOQ221 V7

PRINCIPAL DISPLAY PANEL - Kit Carton - NDC 81520-250

NDC 81520-250-14
Rx only

VOQUEZNA DualPak®
vonoprazan tablets, 20 mg
amoxicillin capsules, 500 mg
Co-packaged for oral use
Carton contains 28 tablets and 84 capsules
14 DAILY TREATMENT PACKS
DUAL THERAPY
Phathom®
PHARMACEUTICALS

PRINCIPAL DISPLAY PANEL - Kit Carton - NDC 81520-255

NDC 81520-255-14

Rx only

VOQUEZNA TriplePak®
vonoprazan tablets 20 mg
amoxicillin capsules 500 mg
clarithromycin tablets 500 mg
Co-packaged for oral use
Carton contains 56 tablets and 56 capsules
14 DAILY TREATMENT PACKS
TRIPLE THERAPY
Phathom®
PHARMACEUTICALS